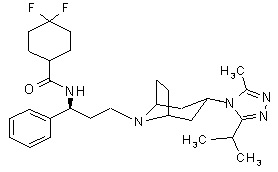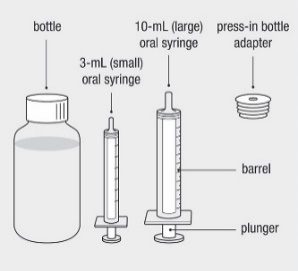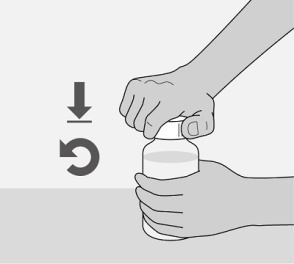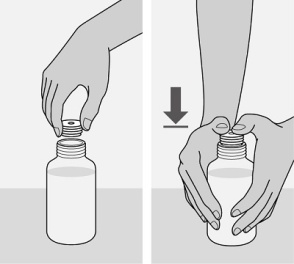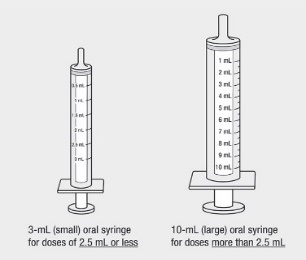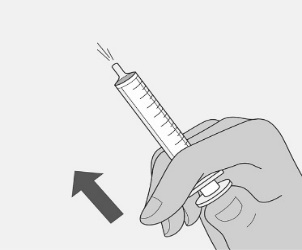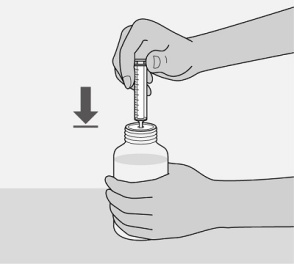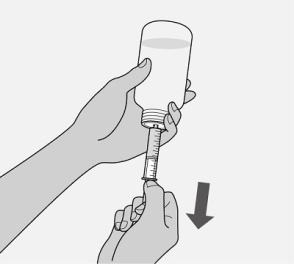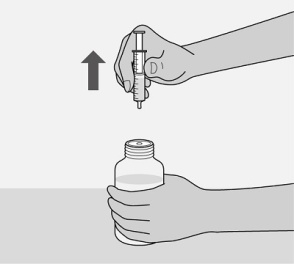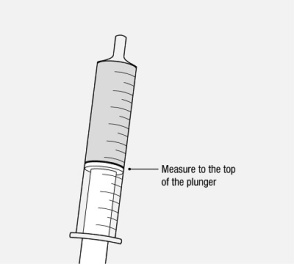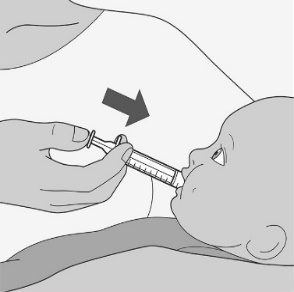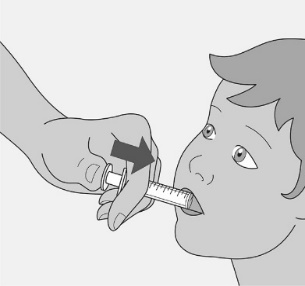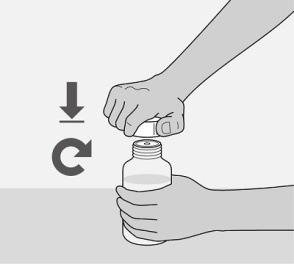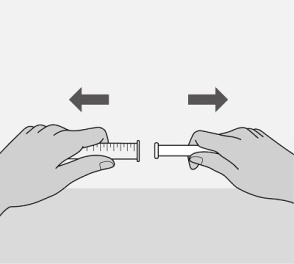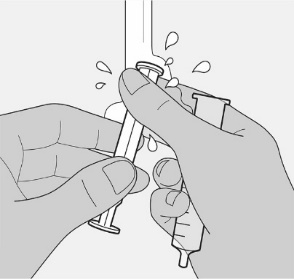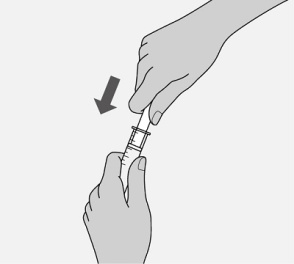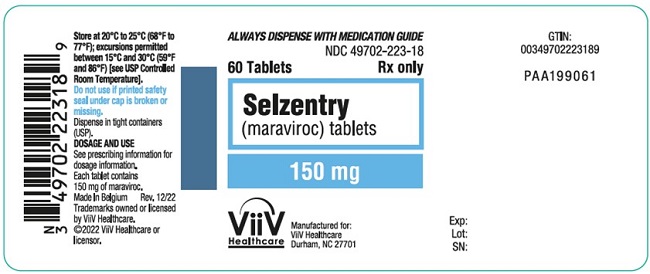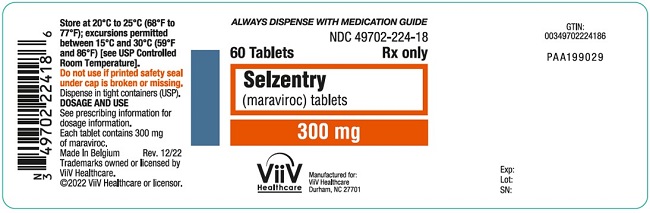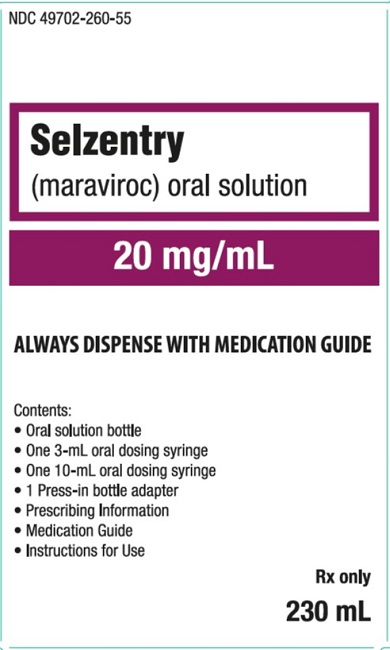 DRUG LABEL: SELZENTRY
NDC: 49702-223 | Form: TABLET, FILM COATED
Manufacturer: ViiV Healthcare Company
Category: prescription | Type: HUMAN PRESCRIPTION DRUG LABEL
Date: 20220926

ACTIVE INGREDIENTS: MARAVIROC 150 mg/1 1
INACTIVE INGREDIENTS: ANHYDROUS DIBASIC CALCIUM PHOSPHATE; MAGNESIUM STEARATE; MICROCRYSTALLINE CELLULOSE; SODIUM STARCH GLYCOLATE TYPE A POTATO; FD&C BLUE NO. 2; ALUMINUM OXIDE; HYDROGENATED SOYBEAN LECITHIN; POLYETHYLENE GLYCOL, UNSPECIFIED; POLYVINYL ALCOHOL, UNSPECIFIED; TALC; TITANIUM DIOXIDE

HIGHLIGHTS OF PRESCRIBING INFORMATION

These highlights do not include all the information needed to use SELZENTRY safely and effectively. See full prescribing information for SELZENTRY.
SELZENTRY (maraviroc) tablets, for oral use
SELZENTRY (maraviroc) oral solution
Initial U.S. Approval: 2007

WARNING: HEPATOTOXICITY

See full prescribing information for complete boxed warning.

- Hepatotoxicity has been reported which may be preceded by severe rash or other features of a systemic allergic reaction (e.g., fever, eosinophilia, or elevated IgE). (5.1)
- Immediately evaluate patients with signs or symptoms of hepatitis or allergic reaction. (5.1)

1 INDICATIONS AND USAGE

SELZENTRY is a CCR5 co-receptor antagonist indicated in combination with other antiretroviral agents for the treatment of only CCR5-tropic HIV-1 infection in adults and pediatric patients weighing at least 2 kg. (1)

Limitations of Use:

- Not recommended in patients with dual/mixed- or CXCR4-tropic HIV-1. (1)

2 DOSAGE AND ADMINISTRATION

- Prior to initiation of SELZENTRY for treatment of HIV-1 infection, test all patients for CCR5 tropism using a highly sensitive tropism assay. (2.1)
- SELZENTRY tablets and oral solution are taken twice daily by mouth and may be taken with or without food. SELZENTRY must be given in combination with other antiretroviral medications. (2.2)

Recommended Dosage in Adult Patients: (2.3)

Concomitant Medications | Dosage of SELZENTRY
When given with potent cytochrome P450 (CYP)3A inhibitors (with or without potent CYP3A inducers) including PIs (except tipranavir/ritonavir) (2.3, 7.1) | 150 mg; twice daily
With NRTIs, tipranavir/ritonavir, nevirapine, raltegravir, and other drugs that are not potent CYP3A inhibitors or CYP3A inducers (2.3, 7.1) | 300 mg; twice daily
With potent and moderate CYP3A inducers including efavirenz (without a potent CYP3A inhibitor) (2.3, 7.1) | 600 mg; twice daily

A more complete list of coadministered drugs is listed in Dosage and Administration. (2)

Recommended Dosage in Pediatric Patients Weighing at Least 2 kg: Administer twice daily. Dosage should be based on body weight (kg) and concomitant medications and should not exceed the recommended adult dose. (2.4)

Recommended Dosage in Patients with Renal Impairment: Dose adjustment may be necessary in adult patients with renal impairment. (2.5)

3 DOSAGE FORMS AND STRENGTHS

- Tablets: 25 mg, 75 mg, 150 mg and 300 mg. (3)
- Oral Solution: 20 mg per mL (3)

4 CONTRAINDICATIONS

SELZENTRY is contraindicated in patients with severe renal impairment or end-stage renal disease (ESRD) (creatinine clearance [CrCl] less than 30 mL per minute) who are concomitantly taking potent CYP3A inhibitors or inducers. (4)

5 WARNINGS AND PRECAUTIONS

- Hepatotoxicity accompanied by severe rash or systemic allergic reaction, including potentially life-threatening events, has been reported. Hepatic laboratory parameters including alanine aminotransferase (ALT), aspartate aminotransferase (AST), and bilirubin should be obtained prior to starting SELZENTRY and at other time points during treatment as clinically indicated. If rash or symptoms or signs of hepatitis or allergic reaction develop, hepatic laboratory parameters should be monitored and discontinuation of treatment should be considered. When administering SELZENTRY to patients with pre-existing liver dysfunction or who are co-infected with hepatitis B and/or C virus, additional monitoring may be warranted. (5.1)
- Severe and potentially life-threatening skin and hypersensitivity reactions have been reported in patients taking SELZENTRY. This includes cases of Stevens-Johnson syndrome, hypersensitivity reaction, and toxic epidermal necrolysis. Immediately discontinue SELZENTRY and other suspected agents if signs or symptoms of severe skin or hypersensitivity reactions develop and monitor clinical status, including liver aminotransferases, closely. (5.2)
- More cardiovascular events, including myocardial ischemia and/or infarction, were observed in treatment-experienced subjects who received SELZENTRY. Additional monitoring may be warranted. (5.3)
- If patients with severe renal impairment or ESRD receiving SELZENTRY (without concomitant CYP3A inducers or inhibitors) experience postural hypotension, the dose of SELZENTRY should be reduced from 300 mg twice daily to 150 mg twice daily. (5.3)

6 ADVERSE REACTIONS

- The most common adverse events in treatment-experienced adult subjects (greater than 8% incidence) which occurred at a higher frequency compared with placebo are upper respiratory tract infections, cough, pyrexia, rash, and dizziness. (6.1)
- The most common adverse events in treatment-naive adult subjects (greater than 8% incidence) which occurred at a higher frequency than the comparator arm are upper respiratory tract infections, bronchitis, flatulence, bloating and distention, upper respiratory tract signs and symptoms, and gastrointestinal atonic and hypomotility disorders. (6.1)
- The most common adverse reactions in treatment-experienced pediatric subjects (greater than or equal to 3% incidence) are vomiting, abdominal pain, diarrhea, nausea, and dizziness. (6.1)

To report SUSPECTED ADVERSE REACTIONS, contact ViiV Healthcare at 1-877-844-8872 or FDA at 1-800-FDA-1088 or www.fda.gov/medwatch.

7 DRUG INTERACTIONS

- Coadministration with CYP3A inhibitors, including protease inhibitors (except tipranavir/ritonavir), will increase the concentration of SELZENTRY. (7.1)
- Coadministration with CYP3A inducers, including efavirenz, may decrease the concentration of SELZENTRY. (7.1)
- Coadministration with St. John’s wort is not recommended. (7.1)

8 USE IN SPECIFIC POPULATIONS

- Lactation: Women infected with HIV should be instructed not to breastfeed due to the potential for HIV transmission. (8.2)

FULL PRESCRIBING INFORMATION

WARNING: HEPATOTOXICITY

Hepatotoxicity has been reported with use of SELZENTRY. Severe rash or evidence of a systemic allergic reaction (e.g., fever, eosinophilia, or elevated IgE) prior to the development of hepatotoxicity may occur. Patients with signs or symptoms of hepatitis or allergic reaction following use of SELZENTRY should be evaluated immediately [see Warnings and Precautions (5.1)].

1 INDICATIONS AND USAGE

SELZENTRY is indicated in combination with other antiretroviral agents for the treatment of only CCR5‑tropic human immunodeficiency virus type 1 (HIV‑1) infection in adult and pediatric patients weighing at least 2 kg.

Limitations of Use

- SELZENTRY is not recommended in patients with dual/mixed- or CXCR4-tropic HIV-1 [see Microbiology (12.4)].

2 DOSAGE AND ADMINISTRATION

2.1 Testing prior to Initiation of SELZENTRY

Prior to initiation of SELZENTRY for treatment of HIV-1 infection, test all patients for CCR5 tropism using a highly sensitive tropism assay. SELZENTRY is recommended for patients with only CCR5-tropic HIV-1 infection. Outgrowth of pre-existing low-level CXCR4- or dual/mixed-tropic HIV-1 not detected by tropism testing at screening has been associated with virologic failure on SELZENTRY [see Microbiology (12.4), Clinical Studies (14.1)].

Monitor patients for alanine aminotransferase (ALT), aspartate aminotransferase (AST), and bilirubin prior to initiation of SELZENTRY and at other time points during treatment as clinically indicated [see Warnings and Precautions (5.1)].

2.2 General Dosing Recommendations

- SELZENTRY tablets and oral solution are taken twice daily by mouth and may be taken with or without food.
- SELZENTRY must be given in combination with other antiretroviral medications.
- The recommended dosage of SELZENTRY differs based on concomitant medications due to drug interactions.

2.3 Recommended Dosage in Adult Patients with Normal Renal Function

Table 1 displays oral dosage of SELZENTRY based on different concomitant medications [see Drug Interactions (7.1)].

Table 1. Recommended Dosage in Adults
Concomitant Medications | Dosage of SELZENTRY
Potent cytochrome P450 (CYP)3A inhibitors (with or without a potent CYP3A inducer)a | 150 mg twice daily
Noninteracting concomitant medicationsb | 300 mg twice daily
Potent and moderate CYP3A inducers (without a potent CYP3A inhibitor)c | 600 mg twice daily
a Potent CYP3A inhibitors (with or without a potent CYP3A inducer) including: clarithromycin, cobicistat, elvitegravir/ritonavir, itraconazole, ketoconazole, nefazodone, protease inhibitors (except tipranavir/ritonavir), telithromycin.
b Noninteracting concomitant medications include all medications that are not potent CYP3A inhibitors or inducers such as: dolutegravir, enfuvirtide, nevirapine, all nucleoside reverse transcriptase inhibitors (NRTIs), raltegravir, and tipranavir/ritonavir.
c Potent and moderate CYP3A inducers (without a potent CYP3A inhibitor) including: carbamazepine, efavirenz, etravirine, phenobarbital, phenytoin, and rifampin.

2.4 Recommended Dosage in Pediatric Patients with Normal Renal Function

The recommended dosage of SELZENTRY should be based on body weight (kg) and should not exceed the recommended adult dose. The recommended dosage also differs based on concomitant medications due to drug interactions (Table 2 and Table 3) [see Drug Interactions (7.1), Use in Specific Populations (8.4)].

Before prescribing SELZENTRY tablets, assess children for the ability to swallow tablets. If a child is unable to reliably swallow SELZENTRY tablets, the oral solution formulation should be prescribed.

The recommended oral dosage of SELZENTRY tablets in pediatric patients aged 2 years and older weighing at least 10 kg is presented in Table 2.

Table 2. Recommended Dosage in Pediatric Patients Aged 2 Years and Older Weighing at Least 10 kg (Tablets)
Concomitant Medications | Dosage of SELZENTRY Based on Weight
Concomitant Medications | 10 kg to <14 kg | 14 kg to <20 kg | 20 kg to <30 kg | 30 kg to <40 kg | ≥40 kg
Potent CYP3A inhibitors (with or without a CYP3A inducer)a | 50 mg twice daily | 50 mg twice daily | 75 mg twice daily | 100 mg twice daily | 150 mg twice daily
Noninteracting concomitant medicationsb | 150 mg twice daily | 200 mg twice daily | 200 mg twice daily | 300 mg twice daily | 300 mg twice daily
Potent and moderate CYP3A inducers (without a potent CYP3A inhibitor)c | Not recommendedd
a Potent CYP3A inhibitors (with or without a CYP3A inducer) including: clarithromycin, cobicistat, elvitegravir/ritonavir, itraconazole, ketoconazole, nefazodone, protease inhibitors (except tipranavir/ritonavir), telithromycin.
b Noninteracting concomitant medications including all medications that are not potent CYP3A inhibitors or inducers such as: dolutegravir, enfuvirtide, nevirapine, all NRTIs, raltegravir, and tipranavir/ritonavir.
c Potent and moderate CYP3A inducers (without a potent CYP3A inhibitor) including: carbamazepine, efavirenz, etravirine, phenobarbital, phenytoin, and rifampin.
d Insufficient data are available to recommend use.

The recommended oral dosage of SELZENTRY oral solution in pediatric patients weighing at least 2 kg is presented in Table 3.

Table 3. Recommended Dosage in Pediatric Patients Weighing at Least 2 kg (Oral Solution)
Concomitant Medications | Dosage (Volume of Solution) of SELZENTRY Based on Weight
Concomitant Medications | 2 kg to <4 kg | 4 kg to <6 kg | 6 kg to; <10 kg | 10 kg to; <14 kg | 14 kg to <20 kg | 20 kg to <30 kg | 30 kg to <40 kg | ≥40 kg
Potent CYP3A inhibitors (with or without a CYP3A inducer)a | Not recommendedb |  |  | 50 mg (2.5 mL) twice daily | 50 mg (2.5 mL) twice daily | 80 mg (4 mL) twice daily | 100 mg (5 mL) twice daily | 150 mg (7.5 mL) twice daily
Noninteracting concomitant medicationsc | 30 mg (1.5 mL) twice daily | 40 mg (2 mL) twice daily | 100 mg (5 mL) twice daily | 150 mg (7.5 mL) twice daily | 200 mg (10 mL) twice daily | 200 mg (10 mL) twice daily | 300 mg (15 mL) twice daily | 300 mg (15 mL) twice daily
Potent and moderate CYP3A inducers (without a potent CYP3A inhibitor)d | Not recommendedb
a Potent CYP3A inhibitors (with or without a CYP3A inducer) including: clarithromycin, cobicistat, elvitegravir/ritonavir, itraconazole, ketoconazole, nefazodone, protease inhibitors (except tipranavir/ritonavir), telithromycin.
b Insufficient data are available to recommend use.
c Noninteracting concomitant medications including all medications that are not potent CYP3A inhibitors or inducers such as: dolutegravir, enfuvirtide, nevirapine, all NRTIs, raltegravir, and tipranavir/ritonavir.
d Potent and moderate CYP3A inducers (without a potent CYP3A inhibitor) including: carbamazepine, efavirenz, etravirine, phenobarbital, phenytoin, and rifampin.

Administer the oral solution using the included press-in bottle adapter and the appropriate oral dosing syringe: for doses of 2.5 mL or less, use the 3-mL syringe; for doses greater than 2.5 mL, use the 10-mL syringe.

Care should be taken when measuring neonate doses due to the small volumes of oral solution required.

2.5 Recommended Dosage in Patients with Renal Impairment

Adult Patients

Table 4 provides dosing recommendations for patients based on renal function and concomitant medications.

Table 4. Recommended Dosage in Adults Based on Renal Function
Concomitant Medications | Dosage of SELZENTRY Based on Renal Function
Concomitant Medications | Normal; (CrCl >80 mL/min) | Mild; (CrCl >50 and ≤80 mL/min) | Moderate; (CrCl ≥30 and ≤50 mL/min) | Severe; (CrCl <30 mL/min) | End-Stage Renal Disease on Regular Hemodialysis
Potent CYP3A inhibitors (with or without a CYP3A inducer)a | 150 mg twice daily | 150 mg twice daily | 150 mg twice daily | Contra-indicated | Contra-indicated
Noninteracting concomitant medicationsb | 300 mg twice daily | 300 mg twice daily | 300 mg twice daily | 300 mg twice daily | 300 mg twice dailyc
Potent and moderate CYP3A inducers (without a potent CYP3A inhibitor)d | 600 mg twice daily | 600 mg twice daily | 600 mg twice daily | Contra-indicated | Contra-indicated
CrCl = Creatinine clearance.
a Potent CYP3A inhibitors (with or without a CYP3A inducer) including: clarithromycin, cobicistat, elvitegravir/ritonavir, itraconazole, ketoconazole, nefazodone, protease inhibitors (except tipranavir/ritonavir), telithromycin.
b Noninteracting concomitant medications include all medications that are not potent CYP3A inhibitors or inducers such as: dolutegravir, enfuvirtide, nevirapine, all NRTIs, raltegravir, and tipranavir/ritonavir.
c Dosage of SELZENTRY should be reduced to 150 mg twice daily if there are any symptoms of postural hypotension [see Contraindications (4), Warnings and Precautions (5.3)].
d Potent and moderate CYP3A inducers (without a potent CYP3A inhibitor) including: carbamazepine, efavirenz, etravirine, phenobarbital, phenytoin, and rifampin.

Pediatric Patients

There are no data to recommend specific doses of SELZENTRY in pediatric patients with mild or moderate renal impairment [see Use in Specific Populations (8.6)]. Additionally, SELZENTRY is contraindicated for pediatric patients with severe renal impairment or end-stage renal disease (ESRD) on regular hemodialysis who are receiving potent CYP3A inhibitors or inducers [see Contraindications (4)].

3 DOSAGE FORMS AND STRENGTHS

Tablets:

- 25-mg blue, oval, film-coated tablets debossed with “MVC 25” on one side and plain on the other.
- 75-mg blue, oval, film-coated tablets debossed with “MVC 75” on one side and plain on the other.
- 150-mg blue, oval, film-coated tablets debossed with “MVC 150” on one side and plain on the other.
- 300-mg blue, oval, film-coated tablets debossed with “MVC 300” on one side and plain on the other.

Oral Solution:

- 20 mg per mL clear, colorless, strawberry-flavored oral solution.

4 CONTRAINDICATIONS

SELZENTRY is contraindicated in patients with severe renal impairment or ESRD (creatinine clearance [CrCl] less than 30 mL per minute) who are concomitantly taking potent CYP3A inhibitors or inducers [see Warnings and Precautions (5.3)].

5 WARNINGS AND PRECAUTIONS

5.1 Hepatotoxicity

Hepatotoxicity with allergic features including life-threatening events has been reported in clinical trials and postmarketing. Severe rash or evidence of systemic allergic reaction including drug-related rash with fever, eosinophilia, elevated IgE, or other systemic symptoms have been reported in conjunction with hepatotoxicity [see Warnings and Precautions (5.2)]. These events occurred approximately 1 month after starting treatment. Among reported cases of hepatitis, some were observed in the absence of allergic features or with no pre-existing hepatic disease.

Appropriate laboratory testing including ALT, AST, and bilirubin should be conducted prior to initiating therapy with SELZENTRY and at other time points during treatment as clinically indicated. Hepatic laboratory parameters should be obtained in any patient who develops rash, or signs or symptoms of hepatitis, or allergic reaction. Discontinuation of SELZENTRY should be considered in any patient with signs or symptoms of hepatitis, or with increased liver transaminases combined with rash or other systemic symptoms.

When administering SELZENTRY to patients with pre-existing liver dysfunction or who are co-infected with hepatitis B and/or C virus, additional monitoring may be warranted. The safety and efficacy of SELZENTRY have not been specifically studied in patients with significant underlying liver disorders.

5.2 Severe Skin and Hypersensitivity Reactions

Severe, potentially life-threatening skin and hypersensitivity reactions have been reported in patients taking SELZENTRY, in most cases concomitantly with other drugs associated with these reactions. These include cases of Stevens-Johnson syndrome (SJS), toxic epidermal necrolysis (TEN), and drug rash with eosinophilia and systemic symptoms (DRESS) [see Adverse Reactions (6.2)]. The cases were characterized by features including rash, constitutional findings, and sometimes organ dysfunction, including hepatic failure. Discontinue SELZENTRY and other suspected agents immediately if signs or symptoms of severe skin or hypersensitivity reactions develop (including, but not limited to, severe rash or rash accompanied by fever, malaise, muscle or joint aches, blisters, oral lesions, conjunctivitis, facial edema, lip swelling, eosinophilia). Delay in stopping treatment with SELZENTRY or other suspect drugs after the onset of rash may result in a life-threatening reaction. Clinical status, including liver aminotransferases, should be monitored and appropriate therapy initiated.

5.3 Cardiovascular Events

Eleven subjects (1.3%) who received SELZENTRY had cardiovascular events, including myocardial ischemia and/or infarction, during the Phase 3 trials in treatment‑experienced subjects (total exposure 609 patient‑years [300 on SELZENTRY once daily + 309 on SELZENTRY twice daily]), while no subjects who received placebo had such events (total exposure 111 patient‑years). These subjects generally had cardiac disease or cardiac risk factors prior to use of SELZENTRY, and the relative contribution of SELZENTRY to these events is not known.

In the Phase 2b/3 trial in treatment‑naive adult subjects, 3 subjects (0.8%) who received SELZENTRY had events related to ischemic heart disease and 5 subjects (1.4%) who received efavirenz had such events (total exposure 506 and 508 patient‑years for SELZENTRY and efavirenz, respectively).

When SELZENTRY was administered to healthy volunteers at doses higher than the recommended dose, symptomatic postural hypotension was seen at a greater frequency than in placebo. However, when SELZENTRY was given at the recommended dose in HIV-1–infected adult subjects in Phase 3 trials, postural hypotension was seen at a rate similar to placebo (approximately 0.5%).

Patients with cardiovascular comorbidities, risk factors for postural hypotension, or receiving concomitant medication known to lower blood pressure, could be at increased risk of cardiovascular adverse events triggered by postural hypotension. Additional monitoring may be warranted.

Postural Hypotension in Patients with Renal Impairment

An increased risk of postural hypotension may occur in patients with severe renal insufficiency or in those with ESRD due to increased maraviroc exposure in some patients. SELZENTRY should be used in patients with severe renal impairment or ESRD only if they are not receiving a concomitant potent CYP3A inhibitor or inducer. However, the use of SELZENTRY in these patients should only be considered when no alternative treatment options are available. If adult patients with severe renal impairment or ESRD experience any symptoms of postural hypotension while taking 300 mg twice daily, the dose should be reduced to 150 mg twice daily [see Dosage and Administration (2.5)].

5.4 Immune Reconstitution Syndrome

Immune reconstitution syndrome has been reported in patients treated with combination antiretroviral therapy, including SELZENTRY. During the initial phase of combination antiretroviral treatment, patients whose immune systems respond may develop an inflammatory response to indolent or residual opportunistic infections (such as infection with Mycobacterium avium infection, cytomegalovirus, Pneumocystis jirovecii pneumonia [PCP], tuberculosis, or reactivation of Herpes simplex and Herpes zoster), which may necessitate further evaluation and treatment.

Autoimmune disorders (such as Graves’ disease, polymyositis, and Guillain-Barré syndrome) have also been reported to occur in the setting of immune reconstitution; however, the time to onset is more variable, and can occur many months after initiation of treatment.

5.5 Potential Risk of Infection

SELZENTRY antagonizes the CCR5 co-receptor located on some immune cells, and therefore could potentially increase the risk of developing infections. The overall incidence and severity of infection, as well as AIDS-defining category C infections, were comparable in the treatment groups during the Phase 3 adult treatment‑experienced trials of SELZENTRY. While there was a higher rate of certain upper respiratory tract infections reported in the treatment arm receiving SELZENTRY compared with placebo (23% versus 13%), there was a lower rate of pneumonia (2% versus 5%) reported in subjects receiving SELZENTRY. A higher incidence of Herpes virus infections (11 per 100 patient‑years) was also reported in the treatment arm receiving SELZENTRY when adjusted for exposure compared with placebo (8 per 100 patient‑years).

In the Phase 2b/3 trial in treatment‑naive adult subjects, the incidence of AIDS-defining Category C events when adjusted for exposure was 1.8 for SELZENTRY compared with 2.4 for efavirenz per 100 patient‑years of exposure.

Patients should be monitored closely for evidence of infections while receiving SELZENTRY.

5.6 Potential Risk of Malignancy

While no increase in malignancy has been observed with SELZENTRY, due to this drug’s mechanism of action, it could affect immune surveillance and lead to an increased risk of malignancy.

The exposure-adjusted rate for malignancies per 100 patient‑years of exposure in adult treatment‑experienced trials was 4.6 for SELZENTRY compared with 9.3 on placebo. In treatment‑naive adult subjects, the rates were 1.0 and 2.4 per 100 patient‑years of exposure for SELZENTRY and efavirenz, respectively.

Long-term follow-up is needed to more fully assess this risk.

6 ADVERSE REACTIONS

The following adverse reactions are discussed in other sections of the labeling:

- Hepatotoxicity [see Boxed Warning, Warnings and Precautions (5.1)]
- Severe Skin and Hypersensitivity Reactions [see Warnings and Precautions (5.2)]
- Cardiovascular Events [see Warnings and Precautions (5.3)]

6.1 Clinical Trials Experience

Because clinical trials are conducted under widely varying conditions, adverse reaction rates observed in the clinical trials of a drug cannot be directly compared with rates in the clinical trials of another drug and may not reflect the rates observed in practice.

Clinical Trials Experience in Adult Subjects

Treatment‑Experienced Subjects: The safety profile of SELZENTRY is primarily based on 840 HIV-1–infected subjects who received at least 1 dose of SELZENTRY during two Phase 3 trials. A total of 426 of these subjects received the indicated twice‑daily dosing regimen.

Assessment of treatment‑emergent adverse events is based on the pooled data from 2 trials in subjects with CCR5-tropic HIV‑1 (A4001027 and A4001028). The median duration of therapy with SELZENTRY for subjects in these trials was 48 weeks, with the total exposure on SELZENTRY twice daily at 309 patient‑years versus 111 patient‑years on placebo each administered with optimized background therapy (OBT). The population was 89% male and 84% white, with mean age of 46 years (range: 17 to 75 years). Subjects received dose equivalents of 300 mg maraviroc once or twice daily.

The most common adverse events reported with twice‑daily therapy with SELZENTRY with frequency rates higher than placebo, regardless of causality, were upper respiratory tract infections, cough, pyrexia, rash, and dizziness. In these 2 trials, the rate of discontinuation due to adverse events was 5% for subjects who received SELZENTRY twice daily + OBT as well as those who received placebo + OBT. Most of the adverse events reported were judged to be mild to moderate in severity. The data described below occurred with twice‑daily dosing of SELZENTRY.

The total numbers of subjects reporting infections were 233 (55%) and 84 (40%) in the group receiving SELZENTRY twice daily and the placebo group, respectively. Correcting for the longer duration of exposure on SELZENTRY compared with placebo, the exposure‑adjusted frequency (rate per 100 subject‑years) of these events was 133 for both SELZENTRY twice daily and placebo.

Dizziness or postural dizziness occurred in 8% of subjects on either SELZENTRY or placebo, with 2 subjects (0.5%) on SELZENTRY permanently discontinuing therapy (1 due to syncope, 1 due to orthostatic hypotension) versus 1 subject on placebo (0.5%) permanently discontinuing therapy due to dizziness.

Treatment-emergent adverse events, regardless of causality, from Trials A4001027 and A4001028 are summarized in Table 5. Selected events occurring at greater than or equal to 2% of subjects and at a numerically higher rate in subjects treated with SELZENTRY are included; events that occurred at the same or higher rate on placebo are not displayed.

Table 5. Selected Treatment-Emergent Adverse Events (All Causality) ≥2% on SELZENTRY (and at a Higher Rate Compared with Placebo) in Trials A4001027 and A4001028 (Pooled Analysis, 48 Weeks)
 | SELZENTRY; Twice Dailya |  | Placebo
Body System/; Adverse Event | (n = 426); % | Exposure-Adjusted Rate; (per 100 pt-yrs); PYE = 309b | (n = 209); % | Exposure-Adjusted Rate; (per 100 pt-yrs); PYE = 111b
Eye Disorders
Conjunctivitis | 2 | 3 | 1 | 3
Ocular infections, inflammations, and associated manifestations | 2 | 3 | 1 | 2
Gastrointestinal Disorders
Constipation | 6 | 9 | 3 | 6
General Disorders and Administration Site Conditions
Pyrexia | 13 | 20 | 9 | 17
Pain and discomfort | 4 | 5 | 3 | 5
Infections and Infestations
Upper respiratory tract infection | 23 | 37 | 13 | 27
Herpes infection | 8 | 11 | 4 | 8
Sinusitis | 7 | 10 | 3 | 6
Bronchitis | 7 | 9 | 5 | 9
Folliculitis | 4 | 5 | 2 | 4
Anogenital warts | 2 | 3 | 1 | 3
Influenza | 2 | 3 | 0.5 | 1
Otitis media | 2 | 3 | 0.5 | 1
Metabolism and Nutrition Disorders
Appetite disorders | 8 | 11 | 7 | 13
Musculoskeletal and Connective Tissue Disorders
Joint-related signs and symptoms | 7 | 10 | 3 | 5
Muscle pains | 3 | 4 | 0.5 | 1
Neoplasms Benign, Malignant, and Unspecified
Skin neoplasms benign | 3 | 4 | 1 | 3
Nervous System Disorders
Dizziness/postural dizziness | 9 | 13 | 8 | 17
Paresthesias and dysesthesias | 5 | 7 | 3 | 6
Sensory abnormalities | 4 | 6 | 1 | 3
Disturbances in consciousness | 4 | 5 | 3 | 6
Peripheral neuropathies | 4 | 5 | 3 | 6
Psychiatric Disorders
Disturbances in initiating and maintaining sleep | 8 | 11 | 5 | 10
Depressive disorders | 4 | 6 | 3 | 5
Anxiety symptoms | 4 | 5 | 3 | 7
Renal and Urinary Disorders
Bladder and urethral symptoms | 5 | 7 | 1 | 3
Urinary tract signs and symptoms | 3 | 4 | 1 | 3
Respiratory, Thoracic, and Mediastinal Disorders
Coughing and associated symptoms | 14 | 21 | 5 | 10
Upper respiratory tract signs and symptoms | 6 | 9 | 3 | 6
Nasal congestion and inflammations | 4 | 6 | 3 | 5
Breathing abnormalities | 4 | 5 | 2 | 5
Paranasal sinus disorders | 3 | 4 | 0.5 | 1
Skin and Subcutaneous Tissue Disorders
Rash | 11 | 16 | 5 | 11
Apocrine and eccrine gland disorders | 5 | 7 | 4 | 7.5
Pruritus | 4 | 5 | 2 | 4
Lipodystrophies | 3 | 5 | 0.5 | 1
Erythema | 2 | 3 | 1 | 2
Vascular Disorders
Vascular hypertensive disorders | 3 | 4 | 2 | 4
a 300-mg dose equivalent.
b PYE = Patient-years of exposure.

Laboratory Abnormalities: Table 6 shows the treatment-emergent Grade 3-4 laboratory abnormalities that occurred in greater than 2% of subjects receiving SELZENTRY.

Table 6. Maximum Shift in Laboratory Test Values (without Regard to Baseline) ≥2% of Grade 3-4 Abnormalities (ACTG Criteria) in Trials A4001027 and A4001028 (Pooled Analysis, 48 Weeks)
Laboratory Parameter Preferred Term | Limit | SELZENTRY; Twice Daily + OBT; (n = 421)a; % | Placebo + OBT; (n = 207)a; %
Aspartate aminotransferase | >5.0 x ULN | 4.8 | 2.9
Alanine aminotransferase | >5.0 x ULN | 2.6 | 3.4
Total bilirubin | >2.5 x ULN | 5.5 | 5.3
Amylase | >2.0 x ULN | 5.7 | 5.8
Lipase | >2.0 x ULN | 4.9 | 6.3
Absolute neutrophil count | <750/mm^3 | 4.3 | 2.4
ULN = Upper limit of normal; OBT = Optimized background therapy.
a Percentages based on total subjects evaluated for each laboratory parameter.

Treatment‑Naive Subjects: Treatment-Emergent Adverse Events: Treatment-emergent adverse events, regardless of causality, from Trial A4001026, a double-blind, comparative, controlled trial in which 721 treatment-naive subjects received SELZENTRY 300 mg twice daily (n = 360) or efavirenz 600 mg once daily (n = 361) in combination with lamivudine/zidovudine (COMBIVIR) for 96 weeks, are summarized in Table 7. Selected events occurring in greater than or equal to 2% of subjects and at a numerically higher rate in subjects treated with SELZENTRY are included; events that occurred at the same or higher rate on efavirenz are not displayed.

Table 7. Selected Treatment-Emergent Adverse Events (All Causality) ≥2% on SELZENTRY (and at a Higher Rate Compared with Efavirenz) in Trial A4001026 (96 Weeks)
Body System/; Adverse Event | SELZENTRY 300 mg Twice Daily +; Lamivudine/Zidovudine; (n = 360); % | Efavirenz 600 mg Once Daily +; Lamivudine/Zidovudine; (n = 361); %
Blood and Lymphatic System Disorders
Anemias NEC | 8 | 5
Neutropenias | 4 | 3
Ear and Labyrinth Disorders
Ear disorders NEC | 3 | 2
Gastrointestinal Disorders
Flatulence, bloating, and distention | 10 | 7
Gastrointestinal atonic and hypomotility disorders NEC | 9 | 5
Gastrointestinal signs and symptoms NEC | 3 | 2
General Disorders and Administration Site Conditions
Body temperature perception | 3 | 1
Infections and Infestations
Upper respiratory tract infection | 32 | 30
Bronchitis | 13 | 9
Herpes infection | 7 | 6
Bacterial infections NEC | 6 | 3
Herpes zoster/varicella | 5 | 4
Tinea infections | 4 | 3
Lower respiratory tract and lung infections | 3 | 2
Neisseria infections | 3 | 0
Viral infections NEC | 3 | 2
Musculoskeletal and Connective Tissue Disorders
Joint-related signs and symptoms | 6 | 5
Nervous System Disorders
Paresthesias and dysesthesias | 4 | 3
Memory loss (excluding dementia) | 3 | 1
Renal and Urinary Disorders
Bladder and urethral symptoms | 4 | 3
Reproductive System and Breast Disorders
Erection and ejaculation conditions and disorders | 3 | 2
Respiratory, Thoracic, and Mediastinal Disorders
Upper respiratory tract signs and symptoms | 9 | 5
Skin and Subcutaneous Disorders
Nail and nail bed conditions (excluding infections and infestations) | 6 | 2
Lipodystrophies | 4 | 3
Acnes | 3 | 2
Alopecias | 2 | 1

Laboratory Abnormalities:

Table 8. Maximum Shift in Laboratory Test Values (without Regard to Baseline) ≥2% of Grade 3-4 Abnormalities (ACTG Criteria) in Trial A4001026 (96 Weeks)
Laboratory Parameter Preferred Term | Limit | SELZENTRY; 300 mg Twice Daily +; Lamivudine/Zidovudine (n = 353)a; % | Efavirenz; 600 mg Once Daily+; Lamivudine/Zidovudine (n = 350)a; %
Aspartate aminotransferase | >5.0 x ULN | 4.0 | 4.0
Alanine aminotransferase | >5.0 x ULN | 3.9 | 4.0
Creatine kinase | >10.0 x ULN | 3.9 | 4.8
Amylase | >2.0 x ULN | 4.3 | 6.0
Absolute neutrophil count | <750/mm^3 | 5.7 | 4.9
Hemoglobin | <7.0 g/dL | 2.9 | 2.3
ULN = Upper limit of normal.
a n = Total number of subjects evaluable for laboratory abnormalities.
Percentages based on total subjects evaluated for each laboratory parameter. If the same subject in a given treatment group had greater than 1 occurrence of the same abnormality, only the most severe is counted.

Less Common Adverse Events in Clinical Trials: The following adverse events occurred in less than 2% of subjects treated with SELZENTRY or at a rate similar to the comparator. These events have been included because of their seriousness and either increased frequency on SELZENTRY or are potential risks due to the mechanism of action. Events attributed to the subjects’ underlying HIV-1 infection are not listed.

Blood and Lymphatic System: Marrow depression and hypoplastic anemia.

Cardiac Disorders: Unstable angina, acute cardiac failure, coronary artery disease, coronary artery occlusion, myocardial infarction, myocardial ischemia.

Hepatobiliary Disorders: Hepatic cirrhosis, hepatic failure, cholestatic jaundice, portal vein thrombosis, jaundice.

Infections and Infestations: Endocarditis, infective myositis, viral meningitis, pneumonia, treponema infections, septic shock, Clostridium difficile colitis, meningitis.

Musculoskeletal and Connective Tissue Disorders: Myositis, osteonecrosis, rhabdomyolysis, blood creatine kinase increased.

Neoplasms Benign, Malignant, and Unspecified (Including Cysts and Polyps): Abdominal neoplasm, anal cancer, basal cell carcinoma, Bowen’s disease, cholangiocarcinoma, diffuse large B-cell lymphoma, lymphoma, metastases to liver, esophageal carcinoma, nasopharyngeal carcinoma, squamous cell carcinoma, squamous cell carcinoma of skin, tongue neoplasm (malignant stage unspecified), anaplastic large cell lymphomas T- and null-cell types, bile duct neoplasms malignant, endocrine neoplasms malignant and unspecified.

Nervous System Disorders: Cerebrovascular accident, convulsions and epilepsy, tremor (excluding congenital), facial palsy, hemianopia, loss of consciousness, visual field defect.

Clinical Trials Experience in Pediatric Subjects

HIV-1–Infected Pediatric Subjects: Trial A4001031 is an open-label trial in which 103 treatment-experienced, CCR5-tropic, HIV-1–infected pediatric subjects aged 2 to less than 18 years weighing at least 10 kg received SELZENTRY twice daily in combination with OBT. The dose of SELZENTRY was based on body surface area (BSA) and on whether the subject was receiving potent CYP3A inhibitors and/or inducers. The median duration of therapy with SELZENTRY was 131 weeks with 72% of subjects receiving study treatment for greater than 48 weeks and 62% of subjects receiving study treatment for 96 weeks.

In these 103 children and adolescents, the safety profile through 96 weeks was similar to that for adults. Most of the adverse reactions reported were mild to moderate; severe (Grade 3 and 4) adverse reactions occurred in 2% of subjects. The most common adverse reactions (all grades) reported with twice-daily therapy with SELZENTRY were vomiting (12%), abdominal pain (4%), diarrhea (4%), nausea (4%), and dizziness (3%). Three subjects (3%) discontinued due to adverse events.

Maraviroc-related gastrointestinal adverse events through 48 weeks (nausea, vomiting, diarrhea, constipation, and abdominal pain/cramps) were observed more commonly in subjects who received the SELZENTRY oral solution (21%) compared with those who received SELZENTRY tablets (16%). Subjects were permitted to change formulations after Week 48.

HIV-1–Exposed Neonates: The IMPAACT P2007 trial was an open-label trial in which 47 full-term HIV-1–exposed neonates (born to HIV-1–infected mothers) received at least one dose of SELZENTRY in combination with other antiretrovirals, mostly zidovudine and/or nevirapine [see Clinical Pharmacology (12.3)]. Cohort 1 received 2 single doses of SELZENTRY: the first within 3 days of birth and the second at 7 to 14 days of age. Cohort 2 received SELZENTRY twice daily for 6 weeks beginning within 3 days of birth and continued through Week 6. Both cohorts received SELZENTRY with or without exposure to maternal efavirenz (in utero only in Cohort 1, and both in utero and after birth while breastfeeding in Cohort 2). The population was 51% male and 81% black. All infants were followed for safety through 16 weeks, with a total of 37 infants evaluable for safety.

There were no additional adverse reactions observed in neonates compared with those seen in adults. All adverse reactions reported were mild to moderate. The most common adverse reaction (all grades) reported with SELZENTRY was hemoglobin decreased (14%). One subject (3%) discontinued due to an adverse event (Grade 3 staphylococcal sepsis).

6.2 Postmarketing Experience

The following adverse events have been identified during postapproval use of SELZENTRY. Because these reactions are reported voluntarily from a population of uncertain size, it is not always possible to reliably estimate their frequency or establish a causal relationship to drug exposure.

Skin and Subcutaneous Tissue Disorders

Stevens‑Johnson syndrome (SJS), drug rash with eosinophilia and systemic symptoms (DRESS), toxic epidermal necrolysis (TEN).

7 DRUG INTERACTIONS

7.1 Effect of Concomitant Drugs on the Pharmacokinetics of Maraviroc

Maraviroc is metabolized by CYP3A and is also a substrate for P-glycoprotein (P-gp), organic anion-transporting polypeptide (OATP)1B1, and multidrug resistance-associated protein (MRP)2. The pharmacokinetics of maraviroc are likely to be modulated by inhibitors and inducers of CYP3A and P-gp and may be modulated by inhibitors of OATP1B1 and MRP2. Therefore, a dosage adjustment may be required when maraviroc is coadministered with those drugs [see Dosage and Administration (2.3, 2.4)].

Concomitant use of maraviroc and St. John's wort (Hypericum perforatum) or products containing St. John's wort is not recommended. Coadministration of maraviroc with St. John's wort is expected to substantially decrease maraviroc concentrations and may result in suboptimal levels of maraviroc and lead to loss of virologic response and possible resistance to maraviroc.

Additional drug interaction information is available [see Clinical Pharmacology (12.3)].

8 USE IN SPECIFIC POPULATIONS

8.1 Pregnancy

Pregnancy Exposure Registry

There is a pregnancy exposure registry that monitors pregnancy outcomes in women exposed to SELZENTRY during pregnancy. Physicians are encouraged to register patients by calling the Antiretroviral Pregnancy Registry (APR) at 1-800-258-4263.

Risk Summary

Limited data on the use of SELZENTRY during pregnancy from the APR and case reports are not sufficient to inform a drug-associated risk of birth defects and miscarriage. In animal reproduction studies, no evidence of adverse developmental outcomes was observed with maraviroc. During organogenesis in the rat and rabbit, systemic exposures (AUC) to maraviroc were approximately 20 times (rats) and 5 times (rabbits) the exposure in humans at the recommended 300-mg twice-daily dose. In the rat pre- and post-natal development study, maternal systemic exposure (AUC) to maraviroc was approximately 14 times the exposure in humans at the recommended 300-mg twice-daily dose (see Data).

The estimated background risk of major birth defects and miscarriage for the indicated population is unknown. All pregnancies have a background risk of birth defect, loss, or other adverse outcomes. In the U.S. general population, the estimated background risk of major birth defects and miscarriage in clinically recognized pregnancies is 2% to 4% and 15% to 20%, respectively.

Data

Animal Data: Maraviroc was administered orally to pregnant rats (up to 1,000 mg per kg per day) and rabbits (up to 75 mg per kg per day) on gestation Days 6 to 17 and 7 to 19, respectively. No adverse effects on embryo-fetal development were observed at these dose levels, resulting in exposures (AUC) approximately 20 times (rats) and 5 times (rabbits) higher than human exposures at the recommended daily dose. In the rat pre- and post-natal development study, maraviroc was administered orally at up to 1,000 mg per kg per day on gestation Day 6 to lactation/post-partum Day 20, with development of the offspring (including fertility and reproductive performance) unaffected by maternal administration of maraviroc at an exposure (AUC) approximately 14 times higher than human exposure at the recommended daily dose.

8.2 Lactation

Risk Summary

The Centers for Disease Control and Prevention recommend that HIV‑1–infected mothers in the United States not breastfeed their infants to avoid risking postnatal transmission of HIV‑1 infection.

There are no data on the presence of maraviroc in human milk, the effects on the breastfed infant, or the effects on milk production. When administered to lactating rats, maraviroc was present in milk (see Data). Because of the potential for (1) HIV transmission (in HIV-negative infants), (2) developing viral resistance (in HIV-positive infants), and (3) serious adverse reactions in a breastfed infant similar to those seen in adults, instruct mothers not to breastfeed if they are receiving SELZENTRY.

Data

Maraviroc (and related metabolites) was excreted into the milk of lactating rats following a single oral dose of maraviroc (100 mg per kg) on lactation Day 12, with a maximal milk concentration achieved one hour post-administration at a milk concentration approximately 2.5 times that of maternal plasma concentrations.

8.4 Pediatric Use

The safety and efficacy of SELZENTRY have been established in pediatric patients aged from birth to less than 18 years. The use of SELZENTRY in pediatric patients was supported by pharmacokinetic and safety data described below and by previous demonstration of efficacy in adult patients [see Indications and Usage (1), Dosage and Administration (2.4)].

HIV-1–Infected Pediatric Patients Aged 2 to Less Than 18 Years: The safety, pharmacokinetic profile, and antiviral activity of SELZENTRY were evaluated in treatment-experienced, CCR5-tropic, HIV-1–infected pediatric subjects aged 2 to less than 18 years weighing at least 10 kg in an open-label, multicenter clinical trial, A4001031 [see Adverse Reactions (6.1), Clinical Studies (14.2)]. Pharmacokinetics were evaluated in a total of 98 pediatric subjects: 85 subjects received SELZENTRY and concomitant medications that included potent CYP3A inhibitors with or without potent CYP3A inducers, 10 subjects received SELZENTRY and noninteracting medications (not containing potent CYP3A inhibitors or potent CYP3A inducers), and three subjects received SELZENTRY and medications that included potent CYP3A inducers without potent CYP3A inhibitors [see Clinical Pharmacology (12.3)].

HIV-1–Infected Pediatric Patients Aged Older Than 6 Weeks to Less Than 2 Years: No clinical trials have been conducted in children aged older than 6 weeks to less than 2 years. Dosing recommendations for SELZENTRY in this population when concomitantly receiving noninteracting medications are based on population pharmacokinetic modeling and simulation only [see Dosage and Administration (2.4), Clinical Pharmacology (12.3)].

HIV-1–Infected Neonates Aged from Birth to 6 Weeks: The recommendation of SELZENTRY for the treatment of HIV-1 infection in this pediatric population is based on safety and pharmacokinetic data obtained from clinical trial IMPAACT P2007. In IMPAACT P2007, the safety and pharmacokinetic profiles of SELZENTRY were evaluated in full-term HIV-1–exposed neonates (born to HIV-1–infected mothers) aged from birth through 6 weeks [see Adverse Reactions (6.1)]. Pharmacokinetics were evaluated in 38 of 47 enrolled neonates who received SELZENTRY as a single dose (n = 13) or multiple doses (n = 25) up to 6 weeks of age concomitantly with other antiretrovirals (mostly zidovudine and/or nevirapine) with or without maternal exposure to efavirenz. HIV-1 status was assessed by nucleic acid test at birth, Week 6, and Week 16; all 47 enrolled neonates were HIV-1 negative at completion of the study [see Clinical Pharmacology (12.3)].

There are insufficient data to make dosing recommendations for use of SELZENTRY in pediatric patients concomitantly receiving potent CYP3A inhibitors and weighing less than 10 kg, or in any pediatric patients concomitantly receiving potent CYP3A inducers without a potent CYP3A inhibitor [see Dosage and Administration (2.4, 2.5)].

SELZENTRY is not recommended in pre-term neonates or in pediatric patients weighing less than 2 kg.

8.5 Geriatric Use

There were insufficient numbers of subjects aged 65 and over in the clinical trials to determine whether they respond differently from younger subjects. In general, caution should be exercised when administering SELZENTRY in elderly patients, also reflecting the greater frequency of decreased hepatic and renal function, of concomitant disease and other drug therapies.

8.6 Renal Impairment

Recommended doses of SELZENTRY for adult patients with impaired renal function (CrCl less than or equal to 80 mL per minute) are based on the results of a pharmacokinetic trial conducted in healthy adult subjects with various degrees of renal impairment. Maraviroc has not been studied in pediatric patients with renal impairment. There are no data to recommend specific doses of SELZENTRY in pediatric patients with mild to moderate renal impairment [see Use in Specific Populations (8.4)]. SELZENTRY is contraindicated in pediatric patients with severe renal impairment or ESRD on regular hemodialysis who are receiving potent CYP3A inhibitors [see Contraindications (4)].

The pharmacokinetics of maraviroc in adult subjects with mild and moderate renal impairment was similar to that in subjects with normal renal function [see Clinical Pharmacology (12.3)]. A limited number of adult subjects with mild and moderate renal impairment in the Phase 3 clinical trials (n = 131 and n = 12, respectively) received the same dose of SELZENTRY as that administered to subjects with normal renal function. In these subjects, there was no apparent difference in the adverse event profile for maraviroc compared with subjects with normal renal function.

If adult patients with severe renal impairment or ESRD not receiving a concomitant potent CYP3A inhibitor or inducer experience any symptoms of postural hypotension while taking SELZENTRY 300 mg twice daily, the dose should be reduced to 150 mg twice daily. No trials have been performed in subjects with severe renal impairment or ESRD co-treated with potent CYP3A inhibitors or inducers. Hence, no dose of SELZENTRY can be recommended, and SELZENTRY is contraindicated for these patients [see Dosage and Administration (2.3), Contraindications (4), Warnings and Precautions (5.3), Clinical Pharmacology (12.3)].

8.7 Hepatic Impairment

Maraviroc is principally metabolized by the liver; therefore, when administering this drug to patients with hepatic impairment, maraviroc concentrations may be increased. Maraviroc concentrations are higher when SELZENTRY 150 mg is administered with a potent CYP3A inhibitor compared with following administration of 300 mg without a CYP3A inhibitor, so patients with moderate hepatic impairment who receive SELZENTRY 150 mg with a potent CYP3A inhibitor should be monitored closely for maraviroc-associated adverse events. Maraviroc has not been studied in subjects with severe hepatic impairment or in pediatric patients with any degree of hepatic impairment [see Warnings and Precautions (5.1), Clinical Pharmacology (12.3)].

10 OVERDOSAGE

The highest single dose administered in clinical trials was 1,200 mg. The dose-limiting adverse event was postural hypotension, which was observed at 600 mg. While the recommended dose for SELZENTRY in patients receiving a CYP3A inducer without a CYP3A inhibitor is 600 mg twice daily, this dose is appropriate due to enhanced metabolism.

Prolongation of the QT interval was seen in dogs and monkeys at plasma concentrations 6 and 12 times, respectively, those expected in humans at the intended exposure of 300-mg equivalents twice daily. However, no significant QT prolongation was seen in the trials in treatment-experienced subjects with HIV using the recommended doses of maraviroc, or in a specific pharmacokinetic trial to evaluate the potential of maraviroc to prolong the QT interval [see Clinical Pharmacology (12.2)].

There is no specific antidote for overdose with maraviroc. Treatment of overdose should consist of general supportive measures including keeping the patient in a supine position, careful assessment of patient vital signs, blood pressure, and electrocardiogram.

Administration of activated charcoal may also be used to aid in removal of unabsorbed drug. Hemodialysis had a minimal effect on maraviroc clearance and exposure in a trial in subjects with ESRD [see Clinical Pharmacology (12.3)].

11 DESCRIPTION

SELZENTRY (maraviroc) is a selective, slowly reversible, small molecule antagonist of the interaction between human CCR5 and HIV-1 gp120. Blocking this interaction prevents CCR5-tropic HIV-1 entry into cells.

SELZENTRY film-coated tablets for oral administration contain 25, 75, 150, or 300 mg of maraviroc and the following inactive ingredients: dibasic calcium phosphate (anhydrous), magnesium stearate, microcrystalline cellulose, and sodium starch glycolate. The film coat (Opadry II Blue [85G20583]) contains FD&C blue #2 aluminum lake, soya lecithin, polyethylene glycol (macrogol 3350), polyvinyl alcohol, talc, and titanium dioxide.

SELZENTRY oral solution contains 20 mg per mL of maraviroc and the following inactive ingredients: citric acid (anhydrous), purified water, sodium benzoate, sodium citrate dihydrate, strawberry flavoring (501440T), and sucralose.

Maraviroc is chemically described as 4,4-difluoro-N-{(1S)-3-[exo-3-(3-isopropyl-5-methyl-4H-1,2,4-triazol-4-yl)-8-azabicyclo[3.2.1]oct-8-yl]-1-phenylpropyl}cyclohexanecarboxamide.

The molecular formula is C29H41F2N5O and the structural formula is:

Maraviroc is a white to pale-colored powder with a molecular weight of 513.67. It is highly soluble across the physiological pH range (pH 1.0 to 7.5).

12 CLINICAL PHARMACOLOGY

12.1 Mechanism of Action

Maraviroc is an HIV-1 antiviral drug [see Microbiology (12.4)].

12.2 Pharmacodynamics

Exposure-Response Relationship in Treatment-Experienced Adult Subjects

The relationship between maraviroc, modeled plasma trough concentration (Cmin) (1 to 9 samples per subject taken on up to 7 visits), and virologic response was evaluated in 973 treatment-experienced HIV-1-infected subjects with varied optimized background antiretroviral regimens in Trials A4001027 and A4001028. The Cmin, baseline viral load, baseline CD4^+ cell count, and overall sensitivity score (OSS) were found to be important predictors of virologic success (defined as viral load less than 400 copies per mL at 24 weeks). Table 9 illustrates the proportions of subjects with virologic success (%) within each Cmin quartile for 150-mg twice-daily and 300-mg twice-daily groups.

Table 9. Treatment-Experienced Subjects with Virologic Success by Cmin Quartile (Q1-Q4)
 | 150 mg Twice Daily (with CYP3A Inhibitors) |  |  | 300 mg Twice Daily (without CYP3A Inhibitors)
 | n | Median Cmin | % Subjects with Virologic Success | n | Median Cmin | % Subjects with Virologic Success
Placebo | 160 | - | 30.6 | 35 | - | 28.6
Q1 | 78 | 33 | 52.6 | 22 | 13 | 50.0
Q2 | 77 | 87 | 63.6 | 22 | 29 | 68.2
Q3 | 78 | 166 | 78.2 | 22 | 46 | 63.6
Q4 | 78 | 279 | 74.4 | 22 | 97 | 68.2

Exposure-Response Relationship in Treatment-Naive Adult Subjects

The relationship between maraviroc, modeled plasma trough concentration (Cmin) (1 to 12 samples per subject taken on up to 8 visits), and virologic response was evaluated in 294 treatment-naive HIV–1-infected subjects receiving maraviroc 300 mg twice daily in combination with lamivudine/zidovudine in Trial A4001026. Table 10 illustrates the proportion (%) of subjects with virologic success less than 50 copies per mL at 48 weeks within each Cmin quartile for the 300-mg twice-daily dose.

Table 10. Treatment-Naive Subjects with Virologic Success by Cmin Quartile (Q1-Q4)
 | 300 mg Twice Daily
 | n | Median Cmin | % Subjects with Virologic Success
Q1 | 75 | 23 | 57.3
Q2 | 72 | 39 | 72.2
Q3 | 73 | 56 | 74.0
Q4 | 74 | 81 | 83.8

Eighteen of 75 (24%) subjects in Q1 had no measurable maraviroc concentration on at least one occasion versus 1 of 73 and 1 of 74 in Q3 and Q4, respectively.

Effects on Electrocardiogram

A placebo-controlled, randomized, crossover trial to evaluate the effect on the QT interval of healthy male and female volunteers was conducted with 3 single oral doses of maraviroc and moxifloxacin. The placebo-adjusted mean maximum (upper 1-sided 95% CI) increases in QTc from baseline after 100, 300, and 900 mg of maraviroc were –2 (0), -1 (1), and 1 (3) msec, respectively, and 13 (15) msec for moxifloxacin 400 mg. No subject in any group had an increase in QTc of greater than or equal to 60 msec from baseline. No subject experienced an interval exceeding the potentially clinically relevant threshold of 500 msec.

12.3 Pharmacokinetics

Table 11. Mean Maraviroc Pharmacokinetic Parameters in Adults
Patient Population | Maraviroc Dose | n | AUC12 (ng.h/mL) | Cmax (ng/mL) | Cmin (ng/mL)
Healthy volunteers (Phase 1) | 300 mg twice daily | 64 | 2,908 | 888 | 43.1
Asymptomatic HIV subjects (Phase 2a) | 300 mg twice daily | 8 | 2,550 | 618 | 33.6
Treatment-experienced HIV subjects (Phase 3)a | 300 mg twice daily | 94 | 1,513 | 266 | 37.2
Treatment-experienced HIV subjects (Phase 3)a | 150 mg twice daily; (+ CYP3A inhibitor) | 375 | 2,463 | 332 | 101
Treatment-naive HIV subjects (Phase 2b/3)a | 300 mg twice daily | 344 | 1,865 | 287 | 60
a The estimated exposure is lower compared with other trials possibly due to sparse sampling, food effect, compliance, and concomitant medications.

Absorption

Peak maraviroc plasma concentrations are attained 0.5 to 4 hours following single oral doses of 1 to 1,200 mg administered to uninfected volunteers. The pharmacokinetics of oral maraviroc are not dose proportional over the dose range.

The absolute bioavailability of a 100‑mg dose is 23% and is predicted to be 33% at 300 mg. Maraviroc is a substrate for the efflux transporter P-gp.

Effect of Food on Oral Absorption: Coadministration of a 300‑mg tablet with a high‑fat breakfast reduced maraviroc Cmax and AUC by 33% and coadministration of 75 mg of oral solution with a high-fat breakfast reduced maraviroc AUC by 73% in healthy adult volunteers. Studies with the tablet formulation demonstrated a reduced food effect at higher doses.

There were no food restrictions in the adult trials (using the tablet formulation) or in the pediatric trial (using both tablet and oral solution formulations) that demonstrated the efficacy/antiviral activity and safety of maraviroc [see Clinical Studies (14.1, 14.2)].

Distribution

Maraviroc is bound (approximately 76%) to human plasma proteins, and shows moderate affinity for albumin and alpha‑1 acid glycoprotein. The volume of distribution of maraviroc is approximately 194 L.

Elimination

Metabolism: Trials in humans and in vitro studies using human liver microsomes and expressed enzymes have demonstrated that maraviroc is principally metabolized by the cytochrome P450 system to metabolites that are essentially inactive against HIV‑1. In vitro studies indicate that CYP3A is the major enzyme responsible for maraviroc metabolism. In vitro studies also indicate that polymorphic enzymes CYP2C9, CYP2D6, and CYP2C19 do not contribute significantly to the metabolism of maraviroc.

Maraviroc is the major circulating component (~42% drug‑related radioactivity) following a single oral dose of 300 mg [^14C]-maraviroc. The most significant circulating metabolite in humans is a secondary amine (~22% radioactivity) formed by N‑dealkylation. This polar metabolite has no significant pharmacological activity. Other metabolites are products of mono‑oxidation and are only minor components of plasma drug‑related radioactivity.

Excretion: The terminal half‑life of maraviroc following oral dosing to steady state in healthy subjects was 14 to 18 hours. A mass balance/excretion trial was conducted using a single 300‑mg dose of ^14C-labeled maraviroc. Approximately 20% of the radiolabel was recovered in the urine and 76% was recovered in the feces over 168 hours. Maraviroc was the major component present in urine (mean of 8% dose) and feces (mean of 25% dose). The remainder was excreted as metabolites.

Specific Populations

Patients with Hepatic Impairment: Maraviroc is primarily metabolized and eliminated by the liver. A trial compared the pharmacokinetics of a single 300‑mg dose of SELZENTRY in subjects with mild (Child‑Pugh Class A, n = 8) and moderate (Child‑Pugh Class B, n = 8) hepatic impairment with pharmacokinetics in healthy subjects (n = 8). The mean Cmax and AUC were 11% and 25% higher, respectively, for subjects with mild hepatic impairment, and 32% and 46% higher, respectively, for subjects with moderate hepatic impairment compared with subjects with normal hepatic function. These changes do not warrant a dose adjustment. Maraviroc concentrations are higher when SELZENTRY 150 mg is administered with a potent CYP3A inhibitor compared with following administration of 300 mg without a CYP3A inhibitor, so patients with moderate hepatic impairment who receive SELZENTRY 150 mg with a potent CYP3A inhibitor should be monitored closely for maraviroc‑associated adverse events. The pharmacokinetics of maraviroc have not been studied in subjects with severe hepatic impairment [see Warnings and Precautions (5.1)].

Patients with Renal Impairment: A trial compared the pharmacokinetics of a single 300‑mg dose of SELZENTRY in adult subjects with severe renal impairment (CrCl less than 30 mL per minute, n = 6) and ESRD (n = 6) with healthy volunteers (n = 6). Geometric mean ratios for maraviroc Cmax and AUCinf were 2.4‑fold and 3.2‑fold higher, respectively, for subjects with severe renal impairment, and 1.7‑fold and 2.0‑fold higher, respectively, for subjects with ESRD as compared with subjects with normal renal function in this trial. Hemodialysis had a minimal effect on maraviroc clearance and exposure in subjects with ESRD. Exposures observed in subjects with severe renal impairment and ESRD were within the range observed in previous 300‑mg single‑dose trials of SELZENTRY in healthy volunteers with normal renal function. However, maraviroc exposures in the subjects with normal renal function in this trial were 50% lower than those observed in previous trials. Based on the results of this trial, no dose adjustment is recommended for patients with renal impairment receiving SELZENTRY without a potent CYP3A inhibitor or inducer. However, if patients with severe renal impairment or ESRD experience any symptoms of postural hypotension while taking SELZENTRY 300 mg twice daily, their dose should be reduced to 150 mg twice daily [see Dosage and Administration (2.3), Warnings and Precautions (5.3)].

In addition, the trial compared the pharmacokinetics of multiple‑dose SELZENTRY in combination with saquinavir/ritonavir 1,000/100 mg twice daily (a potent CYP3A inhibitor combination) for 7 days in subjects with mild renal impairment (CrCl greater than 50 and less than or equal to 80 mL per minute, n = 6) and moderate renal impairment (CrCl greater than or equal to 30 and less than or equal to 50 mL per minute, n = 6) with healthy volunteers with normal renal function (n = 6). Subjects received 150 mg of SELZENTRY at different dose frequencies (healthy volunteers – every 12 hours; mild renal impairment – every 24 hours; moderate renal impairment – every 48 hours). Compared with healthy volunteers (dosed every 12 hours), geometric mean ratios for maraviroc AUCtau, Cmax, and Cmin were 50% higher, 20% higher, and 43% lower, respectively, for subjects with mild renal impairment (dosed every 24 hours). Geometric mean ratios for maraviroc AUCtau, Cmax, and Cmin were 16% higher, 29% lower, and 85% lower, respectively, for subjects with moderate renal impairment (dosed every 48 hours) compared with healthy volunteers (dosed every 12 hours). Based on the data from this trial, no adjustment in dose is recommended for patients with mild or moderate renal impairment [see Dosage and Administration (2.3)].

Pediatric Patients: Aged 2 to Less Than 18 Years: The pharmacokinetics of maraviroc were evaluated in CCR5-tropic, HIV-1–infected, treatment-experienced pediatric subjects aged 2 to less than 18 years. In the dose-finding stage of Trial A4001031, doses were administered with food on intensive pharmacokinetic evaluation days and optimized to achieve an average concentration over the dosing interval (Cavg) of greater than 100 ng per mL. Throughout the trial, on non-intensive pharmacokinetic evaluation days maraviroc was taken with or without food. The initial dose of maraviroc was based on BSA and concomitant medication category (i.e., presence of CYP3A inhibitors and/or inducers). The conversion of dosing to a weight (kg)-band basis in children provides comparable exposures with those observed in the trial at the corresponding BSA.

Maraviroc pharmacokinetic parameters in pediatric subjects aged 2 to less than 18 years receiving potent CYP3A inhibitors with or without a potent CYP3A inducer were similar to those observed in adults (Table 12).

Table 12. Maraviroc Pharmacokinetic Parameters in Treatment-Experienced Pediatric Patients Receiving SELZENTRY with Potent CYP3A Inhibitors (with or without a Potent CYP3A Inducer)
Weight | Dose of SELZENTRY | Maraviroc Pharmacokinetic Parametera; Geometric Mean
Weight | Dose of SELZENTRY | AUC12 (ng.h/mL) | Cavg (ng/mL) | Cmax (ng/mL) | Cmin (ng/mL)
10 kg to <20 kg | 50 mg twice daily | 2,349 | 196 | 324 | 78
20 kg to <30 kg | 75 mg twice daily | 3,020 | 252 | 394 | 118
30 kg to <40 kg | 100 mg twice daily | 3,229 | 269 | 430 | 126
≥40 kg | 150 mg twice daily | 4,044 | 337 | 563 | 152
a Model-predicted steady-state pharmacokinetic parameters are presented.

Aged from Birth to Less Than 6 Weeks: The pharmacokinetics of maraviroc were evaluated in 38 of 47 enrolled HIV-1–exposed neonates (born to HIV-1–infected mothers) aged from birth up to 6 weeks [see Adverse Reactions (6.1)]. In the IMPAACT P2007 trial, 13 neonates received weight-based maraviroc dosing as single doses at birth and approximately 7 days, and 25 neonates received maraviroc twice daily up to 6 weeks of age without exposure to potent CYP3A inhibitors and/or inducers. Maraviroc pharmacokinetic parameters in neonates weighing at least 2 kg at birth (Table 13) were similar to those observed in adults. Exposure to maternal efavirenz both in utero (for a minimum of 2 weeks immediately prior to delivery) and after birth while breastfeeding did not have a meaningful impact on maraviroc pharmacokinetic parameters.

Table 13. Maraviroc Pharmacokinetic Parameters in Full-Term Neonates (Birth Up to 6 Weeks of Age) Receiving SELZENTRY with Noninteracting Concomitant Medicationsa
Pharmacokinetic Sampling Time | n | Median Dose (range) | Maraviroc Pharmacokinetic Parameter; Geometric Mean
Pharmacokinetic Sampling Time | n | Median Dose (range) | AUC12 (ng.h/mL) | Cavg (ng/mL) | Cmax (ng/mL) | Cmin (ng/mL)
Day 1 | 13 | 30 mg (20 to 40 mg) single dose | 3,510b | 292 | 380 | -
Week 1 | 25 | 25 mg (20 to 30 mg); twice daily | 1,216 | 101 | 262 | 23
Week 4 | 25 | 30 mg (20 to 40 mg); twice daily | 1,385 | 115 | 295 | 43
a Noninteracting concomitant medications include all medications that are not potent CYP3A inhibitors or inducers.
b AUCinf calculated for single-dose pharmacokinetics.

Clinical pharmacokinetic data with maraviroc in pediatric patients aged older than 6 weeks to less than 2 years are not available and clinical pharmacokinetic data in pediatric patients aged 2 to less than 18 years receiving noninteracting concomitant medications are limited. Based on population pharmacokinetic modeling and simulation, the recommended dosing regimen of SELZENTRY for this population is predicted to result in similar maraviroc exposures when compared with exposures achieved in adults receiving SELZENTRY 300 mg twice daily (with noninteracting concomitant medications) [see Dosage and Administration (2.4)].

Geriatric Patients: Pharmacokinetics of maraviroc have not been fully evaluated in the elderly (aged 65 years and older). Based on population pharmacokinetic analyses, age did not have a clinically relevant effect on maraviroc exposure in subjects up to age 65 years [see Use in Specific Populations (8.5)].

Race and Gender: Based on population pharmacokinetics and 2 clinical CYP3A5 genotype analyses for race, no dosage adjustment is recommended based on race or gender.

Drug Interaction Studies

Effect of Concomitant Drugs on the Pharmacokinetics of Maraviroc: Maraviroc is a substrate of CYP3A and P-gp and hence its pharmacokinetics are likely to be modulated by inhibitors and inducers of these enzymes/transporters. The CYP3A/P-gp inhibitors ketoconazole, lopinavir/ritonavir, ritonavir, darunavir/ritonavir, saquinavir/ritonavir, and atazanavir ± ritonavir all increased the Cmax and AUC of maraviroc (Table 14). The CYP3A and/or P-gp inducers rifampin, etravirine, and efavirenz decreased the Cmax and AUC of maraviroc (Table 14). While not studied, potent CYP3A and/or P-gp inducers carbamazepine, phenobarbital, and phenytoin are expected to decrease maraviroc concentrations. Based on in vitro study results, maraviroc is also a substrate of OATP1B1 and MRP2; its pharmacokinetics may be modulated by inhibitors of these transporters.

Tipranavir/ritonavir (net CYP3A inhibitor/P-gp inducer) did not affect the steady‑state pharmacokinetics of maraviroc (Table 14). Cotrimoxazole and tenofovir did not affect the pharmacokinetics of maraviroc.

Table 14. Effect of Coadministered Agents on the Pharmacokinetics of Maraviroc
Coadministered Drug; and Dose | n | Dose of SELZENTRY | Ratio (90% CI) of Maraviroc Pharmacokinetic Parameters with/without Coadministered Drug; (No Effect = 1.00)
Coadministered Drug; and Dose | n | Dose of SELZENTRY | Cmin | AUCtau | Cmax
CYP3A and/or P-gp Inhibitors
Ketoconazole; 400 mg q.d. | 12 | 100 mg b.i.d. | 3.75; (3.01, 4.69) | 5.00; (3.98, 6.29) | 3.38; (2.38, 4.78)
Ritonavir; 100 mg b.i.d. | 8 | 100 mg b.i.d. | 4.55; (3.37, 6.13) | 2.61; (1.92, 3.56) | 1.28; (0.79, 2.09)
Saquinavir (soft gel capsules) /ritonavir; 1,000 mg/100 mg b.i.d. | 11 | 100 mg b.i.d. | 11.3; (8.96, 14.1) | 9.77; (7.87, 12.14) | 4.78; (3.41, 6.71)
Lopinavir/ritonavir; 400 mg/100 mg b.i.d. | 11 | 300 mg b.i.d. | 9.24; (7.98, 10.7) | 3.95; (3.43, 4.56) | 1.97; (1.66, 2.34)
Atazanavir; 400 mg q.d. | 12 | 300 mg b.i.d. | 4.19; (3.65, 4.80) | 3.57; (3.30, 3.87) | 2.09; (1.72, 2.55)
Atazanavir/ritonavir; 300 mg/100 mg q.d. | 12 | 300 mg b.i.d. | 6.67; (5.78, 7.70) | 4.88; (4.40, 5.41) | 2.67; (2.32, 3.08)
Darunavir/ritonavir; 600 mg/100 mg b.i.d. | 12 | 150 mg b.i.d. | 8.00; (6.35, 10.1) | 4.05; (2.94, 5.59) | 2.29; (1.46, 3.59)
Elvitegravir/ritonavir; 150 mg/100 mg q.d. | 11 | 150 mg b.i.d. | 4.23; (3.47, 5.16) | 2.86; (2.33, 3.51) | 2.15; (1.71, 2.69)
CYP3A and/or P-gp Inducers
Efavirenz; 600 mg q.d. | 12 | 100 mg b.i.d. | 0.55; (0.43, 0.72) | 0.55; (0.49, 0.62) | 0.49; (0.38, 0.63)
Efavirenz; 600 mg q.d. | 12 | 200 mg b.i.d.; (+ efavirenz):; 100 mg b.i.d. (alone) | 1.09; (0.89, 1.35) | 1.15; (0.98, 1.35) | 1.16; (0.87, 1.55)
Rifampicin; 600 mg q.d. | 12 | 100 mg b.i.d. | 0.22; (0.17, 0.28) | 0.37; (0.33, 0.41) | 0.34; (0.26, 0.43)
Rifampicin; 600 mg q.d. | 12 | 200 mg b.i.d.; (+ rifampicin):; 100 mg b.i.d. (alone) | 0.66; (0.54, 0.82) | 1.04; (0.89, 1.22) | 0.97; (0.72, 1.29)
Etravirine; 200 mg b.i.d. | 14 | 300 mg b.i.d. | 0.61; (0.53, 0.71) | 0.47; (0.38, 0.58) | 0.40; (0.28, 0.57)
Nevirapinea; 200 mg b.i.d. (+ lamivudine 150 mg b.i.d., tenofovir 300 mg q.d.) | 8 | 300 mg; single dose | – | 1.01; (0.65, 1.55) | 1.54; (0.94, 2.51)
CYP3A and/or P-gp Inhibitors and Inducers
Lopinavir/ritonavir + efavirenz; 400 mg/100 mg b.i.d. + 600 mg q.d. | 11 | 300 mg b.i.d. | 6.29; (4.72, 8.39) | 2.53; (2.24, 2.87) | 1.25; (1.01, 1.55)
Saquinavir (soft gel capsules) /ritonavir + efavirenz 1,000 mg/100 mg b.i.d. + 600 mg q.d. | 11 | 100 mg b.i.d. | 8.42; (6.46, 10.97) | 5.00; (4.26, 5.87) | 2.26; (1.64, 3.11)
Darunavir/ritonavir + etravirine; 600 mg/100 mg b.i.d. + 200 mg b.i.d. | 10 | 150 mg b.i.d. | 5.27; (4.51, 6.15) | 3.10; (2.57, 3.74) | 1.77; (1.20, 2.60)
Fosamprenavir/ritonavir; 700 mg/100 mg b.i.d. | 14 | 300 mg b.i.d. | 4.74; (4.03, 5.57) | 2.49; (2.19, 2.82) | 1.52; (1.27, 1.82)
Fosamprenavir/ritonavir; 1,400 mg/100 mg q.d. | 14 | 300 mg q.d. | 1.80; (1.53, 2.13) | 2.26; (1.99, 2.58) | 1.45; (1.20, 1.74)
Tipranavir/ritonavir; 500 mg/200 mg b.i.d. | 12 | 150 mg b.i.d. | 1.80; (1.55, 2.09) | 1.02; (0.85, 1.23) | 0.86; (0.61, 1.21)
Other
Raltegravir; 400 mg b.i.d. | 17 | 300 mg b.i.d. | 0.90; (0.85, 0.96) | 0.86; (0.80, 0.92) | 0.79; (0.67, 0.94)
a Compared with historical data.

Effect of Maraviroc on the Pharmacokinetics of Concomitant Drugs: Maraviroc is unlikely to inhibit the metabolism of coadministered drugs metabolized by the following cytochrome P enzymes (CYP1A2, CYP2B6, CYP2C8, CYP2C9, CYP2C19, and CYP3A) or to inhibit the uptake of OATP1B1 or the export of MRP2 because maraviroc did not inhibit activity of those enzymes or transporters at clinically relevant concentrations in vitro. Maraviroc does not induce CYP1A2 in vitro. Additionally, in vitro studies have shown that maraviroc is not a substrate for, and does not inhibit, any of the major renal uptake inhibitors (organic anion transporter [OAT]1, OAT3, organic cation transporter [OCT]2, novel organic cation transporter [OCTN]1, and OCTN2) at clinically relevant concentrations.

In vitro results suggest that maraviroc could inhibit P-gp in the gut. However, maraviroc did not significantly affect the pharmacokinetics of digoxin in vivo, indicating maraviroc may not significantly inhibit or induce P-gp clinically.

Drug interaction trials were performed with maraviroc and other drugs likely to be coadministered or commonly used as probes for pharmacokinetic interactions (Table 14).

Coadministration of fosamprenavir 700 mg/ritonavir 100 mg twice daily and maraviroc 300 mg twice daily decreased the Cmin and AUC of amprenavir by 36% and 35%, respectively. Coadministration of fosamprenavir 1,400 mg/ritonavir 100 mg once daily and maraviroc 300 mg once daily decreased the Cmin and AUC of amprenavir by 15% and 30%, respectively. No dosage adjustment is necessary when SELZENTRY is dosed 150 mg twice daily in combination with fosamprenavir/ritonavir dosed once or twice daily. Fosamprenavir should be given with ritonavir when coadministered with SELZENTRY.

Maraviroc had no significant effect on the pharmacokinetics of elvitegravir, zidovudine, or lamivudine. Maraviroc decreased the Cmin and AUC of raltegravir by 27% and 37%, respectively, which is not clinically significant. Maraviroc had no clinically relevant effect on the pharmacokinetics of midazolam, the oral contraceptives ethinylestradiol and levonorgestrel, no effect on the urinary 6β-hydroxycortisol/cortisol ratio, suggesting no induction of CYP3A in vivo. Maraviroc had no effect on the debrisoquine metabolic ratio (MR) at 300 mg twice daily or less in vivo and did not cause inhibition of CYP2D6 in vitro until concentrations greater than 100 microM. However, there was 234% increase in debrisoquine MR on treatment compared with baseline at 600 mg once daily, suggesting potential inhibition of CYP2D6 at higher doses.

12.4 Microbiology

Mechanism of Action

Maraviroc is a member of a therapeutic class called CCR5 co-receptor antagonists. Maraviroc selectively binds to the human chemokine receptor CCR5 present on the cell membrane, preventing the interaction of HIV-1 gp120 and CCR5 necessary for CCR5-tropic HIV-1 to enter cells. CXCR4-tropic and dual-tropic HIV-1 entry is not inhibited by maraviroc.

Antiviral Activity in Cell Culture

Maraviroc inhibits the replication of CCR5-tropic laboratory strains and primary isolates of HIV-1 in models of acute peripheral blood leukocyte infection. The mean EC50 value (50% effective concentration) for maraviroc against HIV-1 group M isolates (subtypes A to J and circulating recombinant form AE) and group O isolates ranged from 0.1 to 4.5 nM (0.05 to 2.3 ng per mL) in cell culture.

When used with other antiretroviral agents in cell culture, the combination of maraviroc was not antagonistic with non-nucleoside reverse transcriptase inhibitors (NNRTIs: efavirenz and nevirapine), NRTIs (abacavir, didanosine, emtricitabine, lamivudine, stavudine, tenofovir, zalcitabine, and zidovudine), or protease inhibitors (PIs: amprenavir, atazanavir, darunavir, indinavir, lopinavir, nelfinavir, ritonavir, saquinavir, and tipranavir). Maraviroc was not antagonistic with the HIV-1 gp41 fusion inhibitor enfuvirtide. Maraviroc was not active against CXCR4-tropic and dual-tropic viruses (EC50 value greater than 10 microM). The antiviral activity of maraviroc against HIV-2 has not been evaluated.

Resistance in Cell Culture: HIV-1 variants with reduced susceptibility to maraviroc have been selected in cell culture following serial passage of 2 CCR5-tropic viruses (CCl/85 and RU570). The maraviroc-resistant viruses remained CCR5-tropic with no evidence of a change from a CCR5-tropic virus to a CXCR4-using virus. Two amino acid residue substitutions in the V3-loop region of the HIV-1 envelope glycoprotein (gp160), A316T, and I323V (HXB2 numbering), were shown to be necessary for the maraviroc-resistant phenotype in the HIV-1 isolate CCl/85. In the RU570 isolate a 3-amino acid residue deletion in the V3 loop, ΔQAI (HXB2 positions 315 to 317), was associated with maraviroc resistance. The relevance of the specific gp120 substitutions observed in maraviroc-resistant isolates selected in cell culture to clinical maraviroc resistance is not known. Maraviroc-resistant viruses were characterized phenotypically by concentration-response curves that did not reach 100% inhibition in phenotypic drug assays, rather than increases in EC50 values.

Cross-Resistance in Cell Culture: Maraviroc had antiviral activity against HIV‑1 clinical isolates resistant to NNRTIs, NRTIs, PIs, and the gp41 fusion inhibitor enfuvirtide in cell culture (EC50 values ranged from 0.7 to 8.9 nM [0.36 to 4.57 ng per mL]). Maraviroc‑resistant viruses that emerged in cell culture remained susceptible to enfuvirtide and the protease inhibitor saquinavir.

Clinical Resistance: Virologic failure on maraviroc can result from genotypic and phenotypic resistance to maraviroc, through outgrowth of undetected CXCR4-using virus present before maraviroc treatment (see Tropism), through resistance to background therapy drugs (Table 15), or due to low exposure to maraviroc [see Clinical Pharmacology (12.2)].

Antiretroviral Treatment-Experienced Adult Subjects (Trials A4001027 and A4001028): Week 48 data from treatment-experienced subjects failing maraviroc-containing regimens with CCR5-tropic virus (n = 58) have identified 22 viruses that had decreased susceptibility to maraviroc characterized in phenotypic drug assays by concentration-response curves that did not reach 100% inhibition. Additionally, CCR5-tropic virus from 2 of these treatment-failure subjects had greater than or equal to 3-fold shifts in EC50 values for maraviroc at the time of failure.

Fifteen of these viruses were sequenced in the gp120 encoding region and multiple amino acid substitutions with unique patterns in the heterogeneous V3 loop region were detected. Changes at either amino acid position 308 or 323 (HXB2 numbering) were seen in the V3 loop in 7 of the subjects with decreased maraviroc susceptibility. Substitutions outside the V3 loop of gp120 may also contribute to reduced susceptibility to maraviroc.

Antiretroviral Treatment-Naive Adult Subjects (Trial A4001026): Treatment-naive subjects receiving SELZENTRY had more virologic failures and more treatment-emergent resistance to the background regimen drugs compared with those receiving efavirenz (Table 15).

Table 15. Development of Resistance to Maraviroc or Efavirenz and Background Drugs in Antiretroviral Treatment-Naive Trial A4001026 for Patients with Only CCR5-Tropic Virus at Screening Using Enhanced Sensitivity TROFILE Assay
 | Maraviroc | Efavirenz
Total N in dataset (as-treated) | 273 | 241
Total virologic failures (as-treated) | 85 (31%) | 56 (23%)
Evaluable virologic failures with post baseline genotypic and phenotypic data | 73 | 43
Lamivudine resistance | 39 (53%) | 13 (30%)
Zidovudine resistance | 2 (3%) | 0
Efavirenz resistance | – | 23 (53%)
Phenotypic resistance to maraviroca | 19 (26%) | –
a Includes subjects failing with CXCR4- or dual/mixed-tropism because these viruses are not intrinsically susceptible to maraviroc.

In an as‑treated analysis of treatment‑naive subjects at 96 weeks, 32 subjects failed a maraviroc‑containing regimen with CCR5‑tropic virus and had a tropism result at failure; 7 of these subjects had evidence of maraviroc phenotypic resistance defined as concentration‑response curves that did not reach 95% inhibition. One additional subject had a greater than or equal to 3‑fold shift in the EC50 value for maraviroc at the time of failure. A clonal analysis of the V3 loop amino acid envelope sequences was performed from 6 of the 7 subjects. Changes in V3 loop amino acid sequence differed between each of these different subjects, even for those infected with the same virus clade, suggesting that there are multiple diverse pathways to maraviroc resistance. The subjects who failed with CCR5‑tropic virus and without a detectable maraviroc shift in susceptibility were not evaluated for genotypic resistance.

Of the 32 maraviroc virologic failures failing with CCR5‑tropic virus, 20 (63%) also had genotypic and/or phenotypic resistance to background drugs in the regimen (lamivudine, zidovudine).

Tropism: In both treatment‑experienced and treatment‑naive subjects, detection of CXCR4‑using virus prior to initiation of therapy has been associated with a reduced virologic response to maraviroc.

Antiretroviral Treatment‑Experienced Subjects (Trials A4001027 and A4001028): In the majority of cases, treatment failure on maraviroc was associated with detection of CXCR4‑using virus (i.e., CXCR4- or dual/mixed‑tropic) which was not detected by the tropism assay prior to treatment. CXCR4‑using virus was detected at failure in approximately 55% of subjects who failed treatment on maraviroc by Week 48, as compared with 9% of subjects who experienced treatment failure in the placebo arm. To investigate the likely origin of the on‑treatment CXCR4‑using virus, a detailed clonal analysis was conducted on virus from 20 representative subjects (16 subjects from the maraviroc arms and 4 subjects from the placebo arm) in whom CXCR4‑using virus was detected at treatment failure. From analysis of amino acid sequence differences and phylogenetic data, it was determined that CXCR4‑using virus in these subjects emerged from a low level of pre-existing CXCR4‑using virus not detected by the tropism assay (which is population-based) prior to treatment rather than from a co-receptor switch from CCR5‑tropic virus to CXCR4‑using virus resulting from mutation in the virus.

Detection of CXCR4‑using virus prior to initiation of therapy has been associated with a reduced virological response to maraviroc. Furthermore, subjects failing twice-daily maraviroc at Week 48 with CXCR4‑using virus had a lower median increase in CD4+ cell counts from baseline (+41 cells per mm^3) than those subjects failing with CCR5‑tropic virus (+162 cells per mm^3). The median increase in CD4+ cell count in subjects failing in the placebo arm was +7 cells per mm^3.

Antiretroviral Treatment‑Naive Subjects (Trial A4001026): In a 96‑week trial of antiretroviral treatment‑naive subjects, 14% (12 of 85) who had only CCR5‑tropic virus at screening with an enhanced sensitivity tropism assay (TROFILE) and failed therapy on maraviroc had CXCR4‑using virus at the time of treatment failure. A detailed clonal analysis was conducted in 2 previously antiretroviral treatment‑naive subjects enrolled in a Phase 2a monotherapy trial who had CXCR4‑using virus detected after 10 days’ treatment with maraviroc. Consistent with the detailed clonal analysis conducted in treatment‑experienced subjects, the CXCR4‑using variants appear to emerge from outgrowth of a pre‑existing undetected CXCR4‑using virus. Screening with an enhanced sensitivity tropism assay reduced the number of maraviroc virologic failures with CXCR4- or dual/mixed‑tropic virus at failure to 12 compared with 24 when screening with the original tropism assay. All but one (11 of 12; 92%) of the maraviroc failures failing with CXCR4- or dual/mixed‑tropic virus also had genotypic and phenotypic resistance to the background drug lamivudine at failure and 33% (4 of 12) developed zidovudine-associated resistance substitutions.

Subjects who had only CCR5‑tropic virus at baseline and failed maraviroc therapy with CXCR4‑using virus had a median increase in CD4+ cell counts from baseline of +113 cells per mm^3 while those subjects failing with CCR5‑tropic virus had an increase of +135 cells per mm^3. The median increase in CD4+ cell count in subjects failing in the efavirenz arm was +95 cells per mm^3.

Antiretroviral Treatment‑Experienced Pediatric Subjects (Trial A4001031): In the Week 48 analysis of Trial A4001031 (n = 103), the mechanisms of resistance to maraviroc observed in the treatment-experienced pediatric population were similar to those observed in adult populations: reasons for virologic failure included failing with CXCR4- or dual/mixed-tropic virus, evidence of reduced maraviroc susceptibility as measured by a decrease in maximal percentage inhibition (MPI), and emergence of resistance to background drug in the regimen.

13 NONCLINICAL TOXICOLOGY

13.1 Carcinogenesis, Mutagenesis, Impairment of Fertility

Carcinogenesis

Long-term oral carcinogenicity studies of maraviroc were carried out in rasH2 transgenic mice (6 months) and in rats for up to 96 weeks (females) and 104 weeks (males). No drug-related increases in tumor incidence were found in mice at 1,500 mg per kg per day and in male and female rats at 900 mg per kg per day. The highest exposures in rats were approximately 11 times those observed in humans at the therapeutic dose of 300 mg twice daily for the treatment of HIV-1 infection.

Mutagenesis

Maraviroc was not genotoxic in the reverse mutation bacterial test (Ames test in Salmonella and E. coli), a chromosome aberration test in human lymphocytes, and mouse bone marrow micronucleus test.

Impairment of Fertility

Maraviroc did not impair mating or fertility of male or female rats and did not affect sperm of treated male rats at approximately 20-fold higher exposures (AUC) than in humans given the recommended 300-mg twice-daily dose.

14 CLINICAL STUDIES

14.1 Clinical Studies in Adult Subjects

The clinical efficacy and safety of SELZENTRY are derived from analyses of data from 3 trials in adult subjects infected with CCR5-tropic HIV-1: Trials A4001027 and A4001028 in antiretroviral treatment-experienced adult subjects and Trial A4001026 in treatment-naive subjects. These trials were supported by a 48-week trial in antiretroviral treatment-experienced adult subjects infected with dual/mixed-tropic HIV-1, Trial A4001029.

Trials in CCR5-Tropic, Treatment-Experienced Subjects

Trials A4001027 and A4001028 were double-blind, randomized, placebo-controlled, multicenter trials in subjects infected with CCR5-tropic HIV-1. Subjects were required to have an HIV-1 RNA greater than 5,000 copies per mL despite at least 6 months of prior therapy with at least 1 agent from 3 of the 4 antiretroviral drug classes (greater than or equal to 1 NRTI, greater than or equal to 1 NNRTI, greater than or equal to 2 PIs, and/or enfuvirtide) or documented resistance to at least 1 member of each class. All subjects received an optimized background regimen consisting of 3 to 6 antiretroviral agents (excluding low-dose ritonavir) selected on the basis of the subject’s prior treatment history and baseline genotypic and phenotypic viral resistance measurements. In addition to the optimized background regimen, subjects were then randomized in a 2:2:1 ratio to SELZENTRY 300 mg once daily, SELZENTRY 300 mg twice daily, or placebo. Doses were adjusted based on background therapy as described in Dosage and Administration (2), Table 1.

In the pooled analysis for Trials A4001027 and A4001028, the demographics and baseline characteristics of the treatment groups were comparable (Table 16). Of the 1,043 subjects with a CCR5-tropism result at screening, 7.6% had a dual/mixed-tropism result at the baseline visit 4 to 6 weeks later. This illustrates the background change from CCR5- to dual/mixed-tropism result over time in this treatment-experienced population, prior to a change in antiretroviral regimen or administration of a CCR5 co-receptor antagonist.

Table 16. Demographic and Baseline Characteristics of Subjects in Trials A4001027 and A4001028
 | SELZENTRY; Twice Daily; (n = 426) | Placebo; (n = 209)
Age (years)
Mean (range) | 46.3 (21-73) | 45.7 (29-72)
Sex:
Male | 382 (89.7%) | 185 (88.5%)
Female | 44 (10.3%) | 24 (11.5%)
Race:
White | 363 (85.2%) | 178 (85.2%)
Black | 51 (12.0%) | 26 (12.4%)
Other | 12 (2.8%) | 5 (2.4%)
Region:
U.S. | 276 (64.8%) | 135 (64.6%)
Non-U.S. | 150 (35.2%) | 74 (35.4%)
Subjects with previous enfuvirtide use | 142 (33.3%) | 62 (29.7%)
Subjects with enfuvirtide as part of OBT | 182 (42.7%) | 91 (43.5%)
Baseline plasma HIV-1 RNA (log10 copies/mL)
Mean (range) | 4.85 (2.96-6.88) | 4.86 (3.46-7.07)
Subjects with screening viral load >100,000 copies/mL | 179 (42.0%) | 84 (40.2%)
Baseline CD4+ cell count (cells/mm^3)
Median (range) | 167 (2-820) | 171 (1-675)
Subjects with baseline CD4+ cell count ≤200 cells/mm^3) | 250 (58.7%) | 118 (56.5%)
Subjects with Overall Susceptibility Score (OSS):a
0 | 57 (13.4%) | 35 (16.7%)
1 | 136 (31.9%) | 44 (21.1%)
2 | 104 (24.4%) | 59 (28.2%)
≥3 | 125 (29.3%) | 66 (31.6%)
Subjects with enfuvirtide resistance substitutions | 90 (21.2%) | 45 (21.5%)
Median number of resistance-associated:b
PI substitutions | 10 | 10
NNRTI substitutions | 1 | 1
NRTI substitutions | 6 | 6
NNRTI = Non-nucleoside reverse transcriptase inhibitors; NRTI = nucleoside reverse transcriptase inhibitors; OBT = optimized background therapy; PI = protease inhibitor.
a OSS - Sum of active drugs in OBT based on combined information from genotypic and phenotypic testing.
b Resistance substitutions based on IAS guidelines.^1

The Week 48 results for the pooled Trials A4001027 and A4001028 are shown in Table 17.

Table 17. Outcomes of Randomized Treatment at Week 48 in Trials A4001027 and A4001028
Outcome | SELZENTRY; Twice Daily; (n = 426) | Placebo; (n = 209) | Mean Difference
Mean change from Baseline to Week 48 in HIV-1 RNA (log10 copies/mL) | -1.84 | -0.78 | -1.05
<400 copies/mL at Week 48 | 239 (56%) | 47 (22%) | 34%
<50 copies/mL at Week 48 | 194 (46%) | 35 (17%) | 29%
Discontinuations:
Insufficient clinical response | 97 (23%) | 113 (54%) | –
Adverse events | 19 (4%) | 11 (5%) | –
Other | 27 (6%) | 18 (9%) | –
Subjects with treatment-emergent CDC Category C events | 22 (5%) | 16 (8%) | –
Deaths (during trial or within 28 days of last dose) | 9 (2%)a | 1 (0.5%) | –
a One additional subject died while receiving open-label therapy with SELZENTRY subsequent to discontinuing double-blind placebo due to insufficient response.

After 48 weeks of therapy, the proportions of subjects with HIV-1 RNA less than 400 copies per mL receiving SELZENTRY compared with placebo were 56% and 22%, respectively. The mean changes in plasma HIV-1 RNA from baseline to Week 48 were –1.84 log10 copies per mL for subjects receiving SELZENTRY + OBT compared with –0.78 log10 copies per mL for subjects receiving OBT only. The mean increase in CD4+ cell count was higher on SELZENTRY twice daily + OBT (124 cells per mm^3) than on placebo + OBT (60 cells per mm^3).

Trial in Dual/Mixed-Tropic, Treatment-Experienced Subjects

Trial A4001029 was an exploratory, randomized, double-blind, multicenter trial to determine the safety and efficacy of SELZENTRY in subjects infected with dual/mixed co-receptor tropic HIV-1. The inclusion/exclusion criteria were similar to those for Trials A4001027 and A4001028 above and the subjects were randomized in a 1:1:1 ratio to SELZENTRY once daily, SELZENTRY twice daily, or placebo. No increased risk of infection or HIV-1 disease progression was observed in the subjects who received SELZENTRY. Use of SELZENTRY was not associated with a significant decrease in HIV-1 RNA compared with placebo in these subjects and no adverse effect on CD4+ cell count was noted.

Trial in Treatment-Naive Subjects

Trial A4001026 was a randomized, double-blind, multicenter trial in subjects infected with CCR5-tropic HIV-1 classified by the original TROFILE tropism assay. Subjects were required to have plasma HIV-1 RNA greater than or equal to 2,000 copies per mL and could not have: 1) previously received any antiretroviral therapy for greater than 14 days, 2) an active or recent opportunistic infection or a suspected primary HIV-1 infection, or 3) phenotypic or genotypic resistance to zidovudine, lamivudine, or efavirenz. Subjects were randomized in a 1:1:1 ratio to SELZENTRY 300 mg once daily, SELZENTRY 300 mg twice daily, or efavirenz 600 mg once daily, each in combination with lamivudine/zidovudine. The efficacy and safety of SELZENTRY are based on the comparison of SELZENTRY twice daily versus efavirenz. In a pre-planned interim analysis at 16 weeks, SELZENTRY 300 mg once daily failed to meet the pre-specified criteria for demonstrating non-inferiority and was discontinued.

The demographic and baseline characteristics of the maraviroc and efavirenz treatment groups were comparable (Table 18). Subjects were stratified by screening HIV-1 RNA levels and by geographic region. The median CD4+ cell counts and mean HIV-1 RNA at baseline were similar for both treatment groups.

Table 18. Demographic and Baseline Characteristics of Subjects in Trial A4001026
 | SELZENTRY 300 mg Twice Daily + Lamivudine/Zidovudine; (n = 360) | Efavirenz 600 mg Once Daily + Lamivudine/Zidovudine; (n = 361)
Age (years):
Mean | 36.7 | 37.4
Range | 20-69 | 18-77
Female, n% | 104 (29) | 102 (28)
Race, n%:
White | 204 (57) | 198 (55)
Black | 123 (34) | 133 (37)
Asian | 6 (2) | 5 (1)
Other | 27 (8) | 25 (7)
Median (range) CD4+ cell count (cells/microL) | 241 (5-1,422) | 254 (8-1,053)
Median (range) HIV-1 RNA (log10 copies/mL) | 4.9 (3-7) | 4.9 (3-7)

The treatment outcomes at 96 weeks for Trial A4001026 are shown in Table 19. Treatment outcomes are based on reanalysis of the screening samples using a more sensitive tropism assay, enhanced sensitivity TROFILE HIV tropism assay, which became available after the Week 48 analysis; approximately 15% of the subjects identified as CCR5-tropic in the original analysis had dual/mixed- or CXCR4-tropic virus. Screening with enhanced sensitivity version of the TROFILE tropism assay reduced the number of maraviroc virologic failures with CXCR4- or dual/mixed-tropic virus at failure to 12 compared with 24 when screening with the original TROFILE HIV tropism assay.

Table 19. Trial Outcome (Snapshot) at Week 96 Using Enhanced Sensitivity Assaya
Outcome at Week 96b | SELZENTRY 300 mg Twice Daily + Lamivudine/Zidovudine; (n = 311); n (%) | Efavirenz 600 mg Once Daily +; Lamivudine/Zidovudine; (n = 303); n (%)
Virologic Responders:
(HIV-1 RNA <400 copies/mL) | 199 (64) | 195 (64)
Virologic Failure:
Non-sustained HIV-1 RNA suppression | 39 (13) | 22 (7)
HIV-1 RNA never suppressed | 9 (3) | 1 (<1)
Virologic Responders:
(HIV-1 RNA <50 copies/mL) | 183 (59) | 190 (63)
Virologic Failure:
Non-sustained HIV-1 RNA suppression | 43 (14) | 25 (8)
HIV-1 RNA never suppressed | 21 (7) | 3 (1)
Discontinuations due to:
Adverse events | 19 (6) | 47 (16)
Death | 2 (1) | 2 (1)
Otherc | 43 (14) | 36 (12)
a The total number of subjects (311, 303) in Table 19 represents the subjects who had a CCR5-tropic virus in the reanalysis of screening samples using the more sensitive tropism assay. This reanalysis reclassified approximately 15% of subjects shown in Table 18 as having dual/mixed- or CXCR4-tropic virus. These numbers are different than those presented in Table 18 because the numbers in Table 18 reflect the subjects with CCR5-tropic virus according to the original tropism assay.
b Week 48 results: Virologic responders (less than 400): 228 of 311 (73%) in SELZENTRY, 219 of 303 (72%) in efavirenz;
Virologic responders (less than 50): 213 of 311 (69%) in SELZENTRY, 207 of 303 (68%) in efavirenz.
c Other reasons for discontinuation include lost to follow-up, withdrawn, protocol violation, and other.

The median increase from baseline in CD4+ cell counts at Week 96 was 184 cells per mm^3 for the arm receiving SELZENTRY compared with 155 cells per mm^3 for the efavirenz arm.

14.2 Clinical Studies in Pediatric Subjects

Trial in CCR5-Tropic, Treatment-Experienced Subjects

Trial A4001031 is an open-label, multicenter trial in pediatric subjects aged 2 to less than 18 years infected with only CCR5‑tropic HIV‑1. Subjects were required to have HIV‑1 RNA greater than 1,000 copies per mL at screening. All subjects (n = 103) received SELZENTRY twice daily and OBT. Dosing of SELZENTRY was based on BSA and doses were adjusted based on whether the subject was receiving potent CYP3A inhibitors and/or inducers.

The population was 52% female and 69% black, with mean age of 10 years (range: 2 to 17 years). At baseline, mean plasma HIV-1 RNA was 4.4 log10 copies per mL (range: 2.4 to 6.2 log10 copies per mL), mean CD4+ cell count was 551 cells per mm^3 (range: 1 to 1,654 cells per mm^3), and mean CD4+ percent was 21% (range: 0% to 42%).

At 48 weeks, 48% of subjects treated with SELZENTRY and OBT achieved plasma HIV-1 RNA less than 48 copies per mL and 65% of subjects achieved plasma HIV-1 RNA less than 400 copies per mL. The mean CD4+ cell count (percent) increase from baseline to Week 48 was 247 cells per mm^3 (5%).

15 REFERENCES

1. IAS-USA Drug Resistance Mutations Figures. https://www.iasusa.org/resources/hiv-drug-resistance-mutations

16 HOW SUPPLIED/STORAGE AND HANDLING

SELZENTRY film-coated tablets are available as follows:

25-mg, 75-mg, 150-mg, and 300-mg tablets are blue, biconvex, oval, film-coated tablets debossed with “MVC 25”, “MVC 75”, “MVC 150”, or “MVC 300”, respectively, on one side and plain on the other.

25-mg tablets: Bottle of 120 tablets (NDC 49702-233-08).

75-mg tablets: Bottle of 120 tablets (NDC 49702-235-08).

150-mg tablets: Bottle of 60 tablets (NDC 49702-223-18).

300-mg tablets: Bottle of 60 tablets (NDC 49702-224-18).

SELZENTRY film‑coated tablets should be stored at 20oC to 25oC (68oF to 77oF); excursions permitted between 15oC and 30oC (59oF and 86oF) [see USP Controlled Room Temperature].

SELZENTRY oral solution is a clear, colorless, strawberry-flavored liquid. Each mL of the solution contains 20 mg of maraviroc. It is supplied in a Convenience Combination Kit (NDC 49702-260-55) as follows:

Bottle of 230 mL (NDC 49702-237-48). Each plastic bottle is packaged with one press-in bottle adapter, one 10–mL oral dosing syringe with 0.5–mL gradations, and one 3–mL oral dosing syringe with 0.5–mL gradations. The press-in bottle adapter and oral dosing syringes are not made with natural rubber latex. This product does not require reconstitution.

SELZENTRY oral solution should be stored at 20oC to 25oC (68oF to 77oF); excursions permitted between 15oC and 30oC (59oF and 86oF) [see USP Controlled Room Temperature]. Discard any unused oral solution 60 days after first opening the bottle.

17 PATIENT COUNSELING INFORMATION

Advise the patient to read the FDA-approved patient labeling (Medication Guide and Instructions for Use).

Hepatotoxicity

Inform patients that hepatotoxicity, including life-threatening cases, has been reported with SELZENTRY; therefore, it is important to inform the healthcare professional if patients have underlying hepatitis B or C or elevations in liver-associated tests prior to treatment. Inform patients to stop SELZENTRY and seek medical evaluation immediately if they develop signs or symptoms of hepatitis or allergic reaction following use of SELZENTRY. Advise patients that laboratory tests for liver enzymes and bilirubin will be ordered prior to starting SELZENTRY, at other times during treatment, and if they develop severe rash or signs and symptoms of hepatitis or an allergic reaction on treatment [see Dosage and Administration (2.1), Warnings and Precautions (5.1, 5.2)].

Cardiovascular Events

When administering SELZENTRY in patients with cardiovascular comorbidities, a history of postural hypotension or receiving concomitant medication known to lower blood pressure, advise patients that they may be at increased risk for cardiovascular events. Advise patients to avoid driving or operating machinery if they experience dizziness while taking SELZENTRY [see Warnings and Precautions (5.3)].

Drug Interactions

Advise patients to inform their healthcare provider of concomitant HIV medications as dosage of SELZENTRY may be modified depending on other HIV medications taken with SELZENTRY. Advise patients that coadministration of SELZENTRY with St. John’s wort is not recommended as it can lead to loss of virologic response and possible resistance to SELZENTRY [see Dosage and Administration (2.2), Drug Interactions (7.1)].

Missed Dosage

Inform patients that it is important to take SELZENTRY in combination with other antiretroviral medications on a regular dosing schedule with or without food. Advise patients to avoid missing doses as it can result in development of resistance. Instruct patients that if they miss a dose, to take it as soon as they remember. Advise patients not to double their next dose or take more than the prescribed dose [see Dosage and Administration (2.2)].

Pregnancy

Inform patients that there is insufficient data on the safety of SELZENTRY in pregnancy. Inform patients that there is an antiretroviral pregnancy registry that monitors pregnancy outcomes in women exposed to SELZENTRY during pregnancy [see Use in Specific Populations (8.1)].

Lactation

Instruct women with HIV-1 infection not to breastfeed because HIV-1 can be passed to the baby in breast milk [see Use in Specific Populations (8.2)].

SELZENTRY and COMBIVIR are trademarks owned by or licensed to the ViiV Healthcare group of companies.

TROFILE is a trademark owned by or licensed to Monogram BioSciences, Inc., and is not owned by or licensed to the ViiV Healthcare group of companies. The maker of this brand is not affiliated with and does not endorse the ViiV Healthcare group of companies or its products.

Manufactured for:

ViiV Healthcare

Durham, NC 27701

©2022 ViiV Healthcare group of companies or its licensor.

SEL:16PI

PHARMACIST‑DETACH HERE AND GIVE MEDICATION GUIDE TO PATIENT

_ _ _ _ _ _ _ _ _ _ _ _ _ _ _ _ _ _ _ _ _ _ _ _ _ _ _ _ _ _ _ _ _ _ _ _ _ _ _ _ _ _ _ _ _ _ _ _ _ _ _ _ _

MEDICATION GUIDE

SELZENTRY (sell-ZEN-tree)

(maraviroc)

tablets

SELZENTRY (sell-ZEN-tree)

(maraviroc)

oral solution

What is the most important information I should know about SELZENTRY?

SELZENTRY can cause serious side effects including serious liver problems (liver toxicity). Some people who take SELZENTRY can develop a severe rash or an allergic reaction before liver problems happen and may be life-threatening. Stop taking SELZENTRY and call your healthcare provider right away if you get any of the following signs or symptoms of liver problems:

- an itchy rash on your body (allergic reaction)
- your skin or the white part of your eyes turns yellow (jaundice)
- dark or “tea-colored” urine

- vomiting
- pain, aching, or tenderness on the right side of your stomach area

Your healthcare provider will do blood tests to check your liver before you begin treatment with SELZENTRY and as needed during treatment with SELZENTRY.

What is SELZENTRY?

SELZENTRY is a prescription Human Immunodeficiency Virus-1 (HIV-1) medicine given with other HIV-1 medicines to treat CCR5-tropic HIV-1 infection in adults and children weighing at least 4.4 lb (2 kg).

HIV-1 is the virus that causes Acquired Immune Deficiency Syndrome (AIDS).

Use of SELZENTRY is not recommended in people with dual/mixed- or CXCR4‑tropic HIV‑1.

SELZENTRY should not be used in premature newborns or children weighing less than 4.4 pounds (2 kg).

Do not take SELZENTRY if you have severe kidney problems or are on hemodialysis and are also taking certain other medications.

Before you take SELZENTRY, tell your healthcare provider about all of your medical conditions, including if you:

- have or have had liver problems including hepatitis B or C virus infection.
- have heart problems.
- have kidney problems.
- have low blood pressure or take medicines to lower blood pressure.
- are pregnant or plan to become pregnant. It is not known if SELZENTRY may harm your unborn baby.
  Pregnancy Registry. There is a pregnancy registry for women who take SELZENTRY during pregnancy. The purpose of this registry is to collect information about the health of you and your baby. Talk to your healthcare provider about how you can take part in this registry.
- are breastfeeding or plan to breastfeed. Do not breastfeed if you take SELZENTRY. You should not breastfeed if you have HIV-1 because of the risk of passing HIV-1 to your baby. Talk to your healthcare provider about the best way to feed your baby.

Tell your healthcare provider about all the medicines you take, including prescription and over-the-counter medicines, vitamins, and herbal supplements.

- Some medicines may interact with SELZENTRY. Keep a list of your medicines to show your healthcare provider and pharmacist.
- You can ask your healthcare provider or pharmacist for a list of medicines that interact with SELZENTRY.

Do not start taking a new medicine without telling your healthcare provider. Your healthcare provider can tell you if it is safe to take SELZENTRY with other medicines. Your healthcare provider may need to change your dose of SELZENTRY when you take it with certain medicines. You should not take SELZENTRY if you also take St. John’s wort (Hypericum perforatum).

How should I take SELZENTRY?

- Take SELZENTRY exactly as your healthcare provider tells you.
- Do not change your dose or stop taking SELZENTRY without first talking with your healthcare provider.
- If you miss a dose of SELZENTRY, take it as soon as you remember. Do not take 2 doses at the same time. If you are not sure about your dosing, call your healthcare provider.
- Stay under the care of a healthcare provider during treatment with SELZENTRY.
- Swallow SELZENTRY tablets whole. Do not chew the tablets.
- SELZENTRY may be taken with or without food.
- Your healthcare provider will prescribe a dose of SELZENTRY based on your child’s body weight and other medicines they are taking.
- Tell your healthcare provider if your child has trouble swallowing tablets. SELZENTRY comes as tablets or as a liquid (oral solution).
- SELZENTRY oral solution should be given with the supplied press-in bottle adapter and oral dosing syringe. See the Instructions for Use that comes with SELZENTRY oral solution for information about the right way to take a dose.
- Do not run out of SELZENTRY. The virus in your blood may increase and the virus in your blood may become harder to treat. When your supply starts to run low, get more from your healthcare provider or pharmacy.
- If you take too much SELZENTRY, call your healthcare provider or go to the nearest hospital emergency room right away.

What are the possible side effects of SELZENTRY?

SELZENTRY can cause serious side effects including:

- See “What is the most important information I should know about SELZENTRY?”
- Severe skin rash and allergic reactions. Severe and potentially life-threatening skin reactions and allergic reactions have been reported in some people taking SELZENTRY. If you develop a rash with any of the following symptoms, stop using SELZENTRY and contact your healthcare provider right away:

- fever
- generally ill feeling
- muscle aches
- blisters or sores in your mouth
- blisters or peeling of the skin
- redness or swelling of the eyes
- swelling of the mouth or face or lips

- problems breathing
- yellowing of the skin or whites of your eyes
- dark or tea-colored urine
- pain, aching, or tenderness on the right side below the ribs
- loss of appetite
- nausea/vomiting

- Heart problems including heart attack.
- Low blood pressure when standing up (postural hypotension) that can cause dizziness or fainting. You should avoid driving or operating heavy machinery if you have dizziness during treatment with SELZENTRY.
- Changes in your immune system (Immune Reconstitution Syndrome) can happen when you start taking HIV-1 medicines. Your immune system may get stronger and begin to fight infections that have been hidden in your body for a long time. Tell your healthcare provider right away if you develop new symptoms during treatment with SELZENTRY.
- Possible chance of infection or cancer. SELZENTRY affects other immune system cells and therefore may possibly increase your chance for getting other infections or cancer.

The most common side effects of SELZENTRY in adults include colds and cold-like symptoms, cough, fever, rash, bloating and gas, indigestion, constipation, and dizziness.

The most common side effects of SELZENTRY in children include vomiting, abdominal pain, diarrhea, nausea, and dizziness.

The most common side effect of SELZENTRY in newborns is decreased hemoglobin (protein inside red blood cells).

These are not all the possible side effects of SELZENTRY. Call your doctor for medical advice about side effects. You may report side effects to FDA at 1‑800‑FDA‑1088.

How should I store SELZENTRY?

- Store SELZENTRY tablets and oral solution at room temperature between 68°F to 77°F (20°C to 25°C).
- Throw away any unused oral solution 60 days after first opening the bottle.

Keep SELZENTRY and all medicines out of the reach of children.

General information about the safe and effective use of SELZENTRY

Medicines are sometimes prescribed for purposes other than those mentioned in a Medication Guide. Do not use SELZENTRY for a condition for which it was not prescribed. Do not give SELZENTRY to other people, even if they have the same symptoms that you have. It may harm them.

You can ask your pharmacist or healthcare provider for the information about SELZENTRY that is written for health professionals.

What are the ingredients in SELZENTRY?

Active ingredient: maraviroc

Inactive ingredients:

Tablets: Dibasic calcium phosphate (anhydrous), magnesium stearate, microcrystalline cellulose, and sodium starch glycolate. Tablet film-coating contains: FD&C blue #2 aluminum lake, soya lecithin, polyethylene glycol (macrogol 3350), polyvinyl alcohol, talc, and titanium dioxide.

Oral Solution: Citric acid, purified water, sodium benzoate, sodium citrate dihydrate, strawberry flavoring (501440T), and sucralose.

Manufactured for:

ViiV Healthcare

Durham, NC 27701

SELZENTRY is a trademark owned by or licensed to the ViiV Healthcare group of companies.

©2022 ViiV Healthcare group of companies or its licensor.

SEL:10MG

For more information go to www.selzentry.com.

This Medication Guide has been approved by the U.S. Food and Drug Administration.

Revised: 9/2022

INSTRUCTIONS FOR USE

SELZENTRY (sell-ZEN-tree)

(maraviroc)

oral solution

Read this Instructions for Use before you start taking SELZENTRY oral solution and each time you get a refill. There may be new information. This leaflet does not take the place of talking to your healthcare provider about your medical condition or treatment.

Important information about measuring SELZENTRY oral solution:

Always use the correct oral syringe that comes with your SELZENTRY oral solution to measure your prescribed dose. Ask your healthcare provider or pharmacist to show you which syringe to use and how to measure your prescribed dose if you are not sure.

Each carton of SELZENTRY oral solution contains:

- One 3-mL oral syringe (for doses of 2.5 mL or less)
- One 10-mL oral syringe (for doses more than 2.5 mL)
- 1 press-in bottle adapter
- 1 bottle of SELZENTRY oral solution

Before each use: Wash your hands with soap and water. Place the items from the carton on a clean flat surface.
Step 1. Open the bottle of SELZENTRY oral solution.
Open the bottle by pushing down firmly on the child-resistant cap and turning it counter-clockwise. See Figure A.

Do not throw away the child-resistant cap.

Figure A. Opening the bottle

Step 2. First time use only: Insert the press-in bottle adapter.
Remove the press-in bottle adapter and oral syringe from the plastic overwrap. With the bottle on a flat surface, push the ribbed end of the press-in bottle adapter all the way into the neck of the bottle while holding the bottle firmly. See Figure B.

Note: Do not remove the press-in bottle adapter from the bottle after it is inserted.

Figure B. Inserting the press-in bottle adapter

Step 3. Choose the oral syringe you need and find your prescribed dose on the oral syringe.
Check the dose in milliliters (mL) as prescribed by your healthcare provider. Choose the right syringe for your child’s dose: use the 3-mL (small) syringe for doses of 2.5 mL or less, or the 10-mL (large) syringe for doses more than 2.5 mL. Then find this marking on the oral syringe. See Figure C.

Figure C. Choose the oral syringe you need and find your prescribed dose.

Step 4. Remove air from oral syringe.
Push the oral syringe plunger to the bottom of the barrel of the syringe (toward its tip) to remove excess air. See Figure D.

Figure D. Removing air from oral syringe.

Step 5. Insert the oral syringe.
Insert the oral syringe into the upright bottle through the opening of the press-in bottle adapter until it is firmly in place. See Figure E.

Figure E. Inserting the oral syringe

Step 6. Withdraw the prescribed dose of SELZENTRY from the bottle.
With the oral syringe in place, turn the bottle upside down. Pull back the plunger of the oral syringe until the top of the plunger is even with the markings on the oral syringe for your prescribed dose. See Figure F.

If you see air bubbles in the oral syringe, fully push the plunger in to empty the oral solution back into the bottle. Then withdraw your prescribed dose of oral solution.

Figure F. Withdrawing the oral solution

Step 7. Removing the oral syringe.
Turn the bottle upright and place the bottle on a flat surface. Remove the oral syringe from the bottle adapter and bottle by pulling straight up on the barrel of the oral syringe. See Figure G.

Figure G. Removing the oral syringe

Step 8. Check the dose withdrawn.
Check that the correct dose was drawn up into the oral syringe. See Figure H.

If the dose is not correct, re-insert the oral syringe tip firmly into the bottle adapter. Fully push in the plunger so that the oral solution flows back into the bottle. Repeat Steps 6 and 7.

Figure H. Checking the dose withdrawn.

Step 9. Take the dose of SELZENTRY. See Figure I.
Place the tip of the oral syringe against the inside of the child’s cheek.

Slowly push the plunger all the way down to give all the medicine in the oral syringe. Make sure the child has time to swallow the medicine.

Note: If the prescribed dose is more than 10 mL, you will need to divide the dose. Follow the instructions given to you by your healthcare provider or pharmacist about how to divide the dose and repeat Steps 5 through 9.

Figure I. Taking the dose of SELZENTRY

Step 10. Close the bottle.
Close the bottle tightly by turning the child-resistant cap clockwise, leaving the press-in bottle adapter in place. See Figure J.

Figure J. Closing the bottle

Step 11. Clean the oral syringe.
Rinse the oral syringe with tap water after each use.

Remove the plunger from the barrel by pulling the plunger and the barrel away from each other. See Figure K.

Rinse the plunger and barrel with water. See Figure L.

Allow parts to air dry completely.

Figure K. Removing the plunger from the barrel

Figure L. Rinsing the plunger and barrel

Step 12. Put the oral syringe back together.
When the barrel and plunger are dry, put the oral syringe back together by inserting the plunger into the barrel. See Figure M. Store the oral syringe with the SELZENTRY oral solution.

Do not throw away the oral syringe.

Figure M. Putting the oral syringe back together

How should I store SELZENTRY?

Store SELZENTRY oral solution at room temperature between 68°F to 77°F (20°C to 25°C).

- Throw away any unused oral solution 60 days after first opening the bottle.

Ask your healthcare provider or pharmacist how to dispose of unused oral solution.

Keep SELZENTRY and all medicines out of the reach of children.

Manufactured for:

ViiV Healthcare

Durham, NC 27701

SELZENTRY is a trademark owned by or licensed to the ViiV Healthcare group of companies.

©2022 ViiV Healthcare group of companies or its licensor.

SEL:4IFU

This Instructions for Use has been approved by the U.S. Food and Drug Administration.

Revised: 9/2022

PACKAGE LABEL

PRINICIPAL DISPLAY PANEL

NDC 49702-223-18

Selzentry

(maraviroc) tablets

150 mg

ALWAYS DISPENSE WITH MEDICATION GUIDE

60 Tablets

Rx only

Manufactured for:

ViiV Healthcare

Durham, NC 27701

Store at 20°C to 25°C (68°F to 77°F); excursions permitted between 15°C and 30°C (59°F - 86°F) [see USP Controlled Room Temperature].

Do not use if printed safety seal under cap is broken or missing.

Dispense in tight containers (USP).

DOSAGE AND USE

See prescribing information for dosage information.

Each tablet contains 150 mg of maraviroc.

Made in Belgium

Rev. 12/22

Trademarks owned or licensed by ViiV Healthcare.

©2022 ViiV Healthcare or licensor.

PAA199061

PACKAGE LABEL

PRINICIPAL DISPLAY PANEL

NDC 49702-224-18

Selzentry

(maraviroc) tablets

300 mg

ALWAYS DISPENSE WITH MEDICATION GUIDE

60 Tablets

Rx only

Manufactured for:

ViiV Healthcare

Durham, NC 27701

Store at 20°C to 25°C (68°F to 77°F); excursions permitted between 15°C and 30°C (59°F - 86°F) [see USP Controlled Room Temperature].

Do not use if printed safety seal under cap is broken or missing.

Dispense in tight containers (USP).

DOSAGE AND USE

See prescribing information for dosage information.

Each tablet contains 300 mg of maraviroc.

Made in Belgium

Rev. 12/22

Trademarks owned or licensed by ViiV Healthcare.

©2022 ViiV Healthcare or licensor.

PAA199029

PACKAGE LABEL

PRINICIPAL DISPLAY PANEL

NDC 49702-260-55

Selzentry

(maraviroc) oral solution

20 mg/mL

ALWAYS DISPENSE WITH MEDICATION GUIDE

Contents:

- Oral solution bottle
- One 3-mL oral dosing syringe
- One 10-mL oral dosing syringe
- 1 Press-in bottle adapter
- Prescribing Information
- Medication Guide
- Instructions for Use

Rx only

230 mL

Made in Belgium

©2022 the ViiV Healthcare group of companies or its licensor.

Rev. 12/22

PAA199834